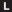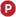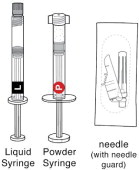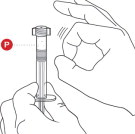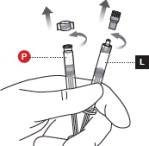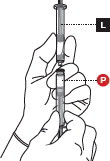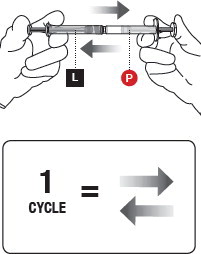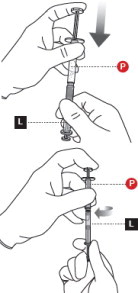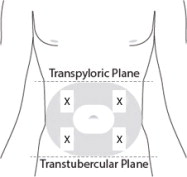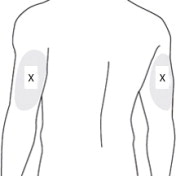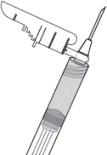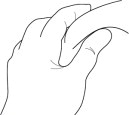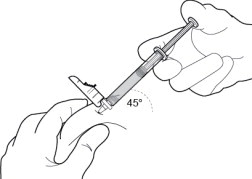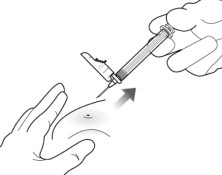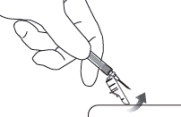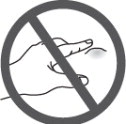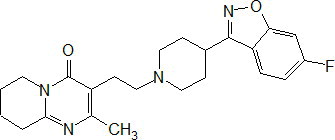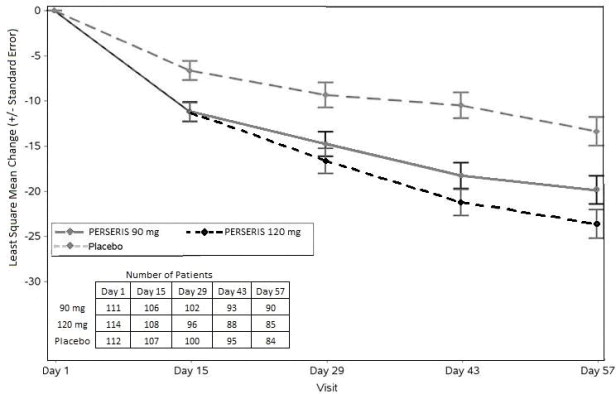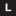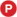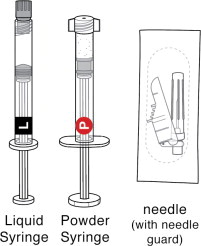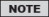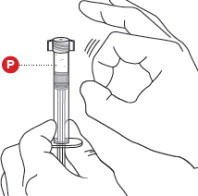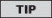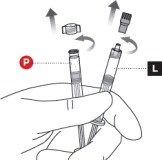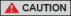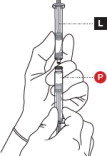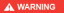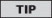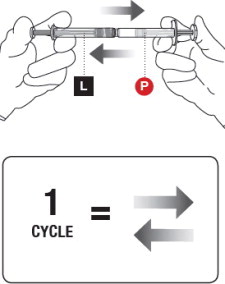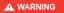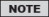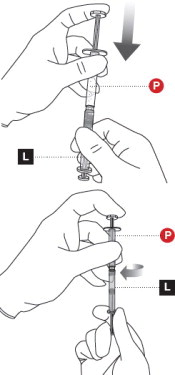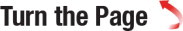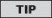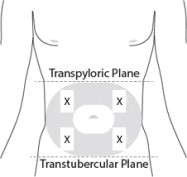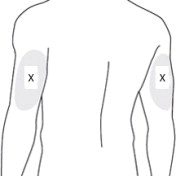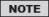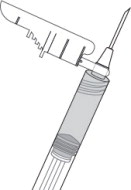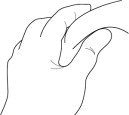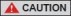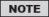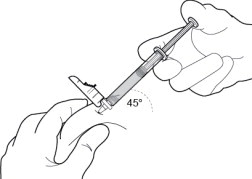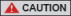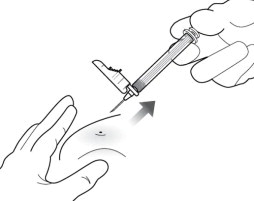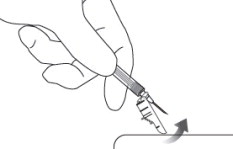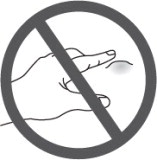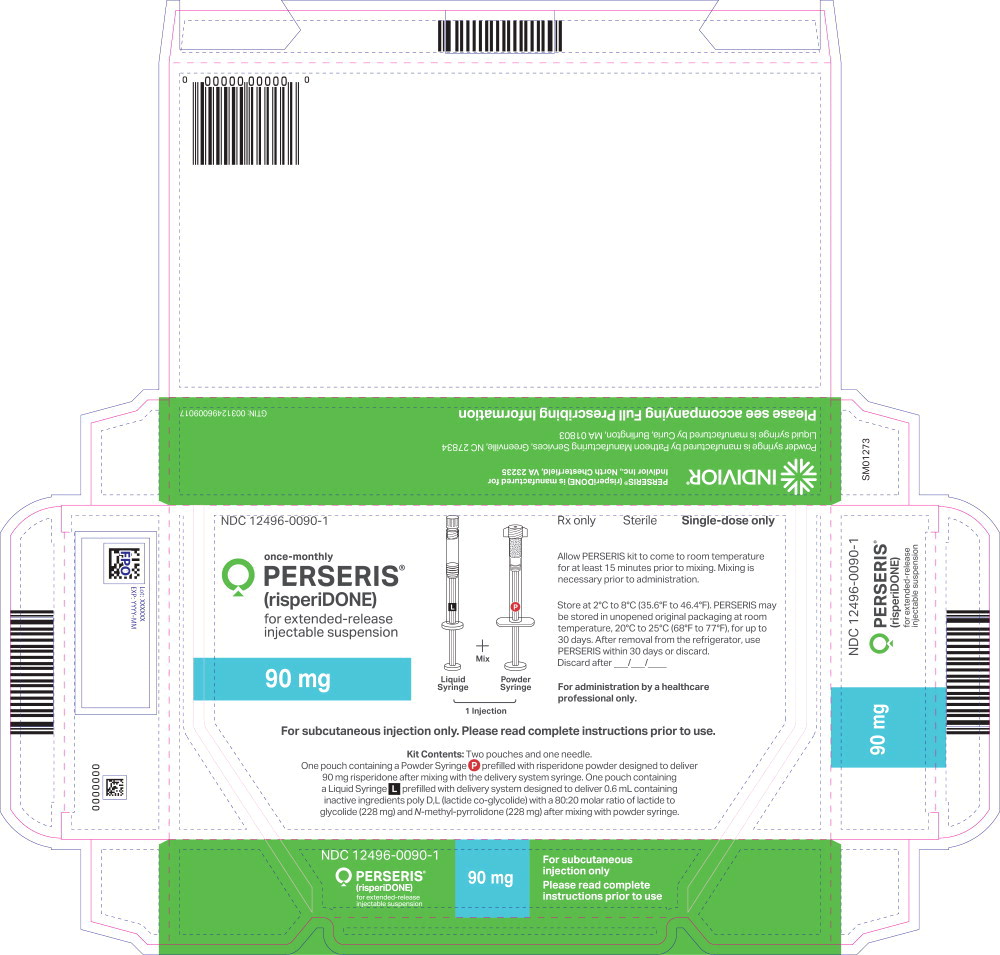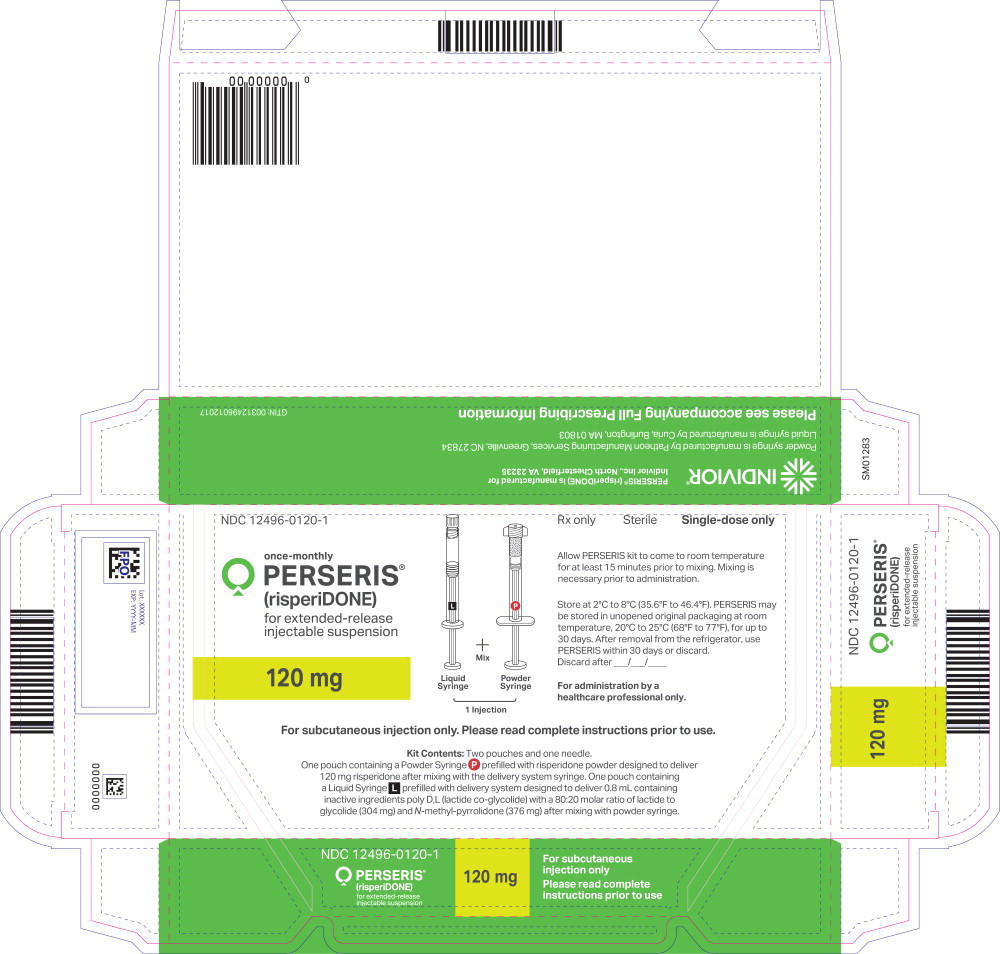 DRUG LABEL: PERSERIS
NDC: 12496-0090 | Form: KIT | Route: SUBCUTANEOUS
Manufacturer: Indivior Inc.
Category: prescription | Type: HUMAN PRESCRIPTION DRUG LABEL
Date: 20250128

ACTIVE INGREDIENTS: RISPERIDONE
 90 mg/0.6 mL
INACTIVE INGREDIENTS: POLY(DL-LACTIC-CO-GLYCOLIC ACID), (50:50; 46000 MW); METHYLPYRROLIDONE

HIGHLIGHTS OF PRESCRIBING INFORMATION

These highlights do not include all the information needed to use PERSERIS®safely and effectively. See full prescribing information for PERSERIS.
PERSERIS (risperidone) for extended-release injectable suspension, for subcutaneous use.
Initial U.S. Approval: 1993

RECENT MAJOR CHANGES

Warnings and Precautions (5.6) | 1/2025

WARNING: INCREASED MORTALITY IN ELDERLY PATIENTS WITH DEMENTIA-RELATED PSYCHOSIS

See full prescribing information for complete boxed warning.

- Elderly patients with dementia-related psychosis treated with antipsychotic drugs are at an increased risk of death.
- PERSERIS is not approved for use in patients with dementia-related psychosis. (5.1)

1 INDICATIONS AND USAGE

PERSERIS is an atypical antipsychotic indicated for the treatment of schizophrenia in adults. (1)

2 DOSAGE AND ADMINISTRATION

- Establish tolerability with oral risperidone prior to initiating PERSERIS. (2.1)
- Administer monthly by subcutaneous injection in the abdomen or back of the upper arm by a healthcare provider. Do not administer by any other route. (2.1)
- PERSERIS may be initiated at a dose of 90 mg or 120 mg once monthly. Do not administer more than one dose per month. (2.1)
- Supplementation with oral risperidone is not recommended. (2.1)
- See Full Prescribing Information for important preparation and administration information. Failure to fully mix the medication could result in incorrect dosage. (2.4)

3 DOSAGE FORMS AND STRENGTHS

For extended-release injectable suspension: 90 mg and 120 mg risperidone. (3)

4 CONTRAINDICATIONS

Known hypersensitivity to risperidone, paliperidone, or other components of PERSERIS. (4)

5 WARNINGS AND PRECAUTIONS

- Cerebrovascular Adverse Reactions, in Elderly Patients with Dementia-Related Psychosis: Increased risk of cerebrovascular adverse reactions (e.g., stroke, transient ischemic attack). (5.2)
- Neuroleptic Malignant Syndrome (NMS): Manage with immediate discontinuation and close monitoring. (5.3)
- Tardive Dyskinesia: Discontinue treatment if clinically appropriate. (5.4)
- Metabolic Changes: Monitor for hyperglycemia, dyslipidemia, and weight gain. (5.5)
- Hyperprolactinemia: Prolactin elevations occur and persist during chronic administration. (5.6)
- Orthostatic Hypotension and Syncope: Monitor heart rate and blood pressure and warn patients with known cardiovascular disease or cerebrovascular disease, and risk of dehydration or syncope. (5.7)
- Leukopenia, Neutropenia, and Agranulocytosis: Perform complete blood counts (CBC) in patients with a history of a clinically significant low white blood cell count (WBC) or history of leukopenia or neutropenia. Consider discontinuing PERSERIS if a clinically significant decline in WBC occurs in absence of other causative factors. (5.9)
- Potential for Cognitive and Motor Impairment: Use caution when operating machinery. (5.10)
- Seizures: Use cautiously in patients with a history of seizures or with conditions that lower the seizure threshold. (5.11)

6 ADVERSE REACTIONS

The most common adverse reactions in clinical trials (≥ 5% and greater than twice placebo) were increased weight, sedation/somnolence, and musculoskeletal pain. (6)

To report SUSPECTED ADVERSE REACTIONS, contact Indivior Inc. at 1-877-782-6966 or FDA at 1-800-FDA-1088 or www.fda.gov/medwatch.

7 DRUG INTERACTIONS

- Carbamazepine and other strong CYP3A4 inducers decrease plasma concentrations of risperidone. (2.3, 7.1)
- Fluoxetine, paroxetine, and other strong CYP2D6 inhibitors increase risperidone plasma concentration. (2.3, 7.1)

8 USE IN SPECIFIC POPULATIONS

- Pregnancy: May cause extrapyramidal and/or withdrawal symptoms in neonates with third trimester exposure. (8.1)
- Renal or Hepatic Impairment: Carefully titrate on oral risperidone up to at least 3 mg before initiating treatment with PERSERIS at a dose of 90 mg. (8.6, 8.7)

FULL PRESCRIBING INFORMATION

WARNING: INCREASED MORTALITY IN ELDERLY PATIENTS WITH DEMENTIA-RELATED PSYCHOSIS

Elderly patients with dementia-related psychosis treated with antipsychotic drugs are at an increased risk of death. PERSERIS® is not approved for the treatment of patients with dementia-related psychosis [see Warnings and Precautions (5.1)].

1 INDICATIONS AND USAGE

PERSERIS is indicated for the treatment of schizophrenia in adults [see Clinical Studies (14)] .

2 DOSAGE AND ADMINISTRATION

2.1 Recommended Dosage

Administer PERSERIS by a healthcare provider as a subcutaneous injection in the abdomen or back of the upper arm. Do not administer PERSERIS by any other route.

For detailed preparation and administration instructions, see Dosage and Administration (2.4) .

For patients who have never taken risperidone, establish tolerability with oral risperidone prior to initiating PERSERIS.

Initiate PERSERIS at a dose of 90 mg or 120 mg once monthly by subcutaneous injection. Do not administer more than one dose (90 mg or 120 mg total) per month.

For patients switching from oral risperidone:

- 3 mg of oral risperidone per day, administer a 90 mg PERSERIS dose one day after the last oral risperidone dose.
- 4 mg of oral risperidone per day, administer a 120 mg PERSERIS dose one day after the last oral risperidone dose.

Patients who are on stable oral risperidone doses lower than 3 mg per day or higher than 4 mg per day may not be candidates for PERSERIS [see Clinical Pharmacology (12.3) and Clinical Studies (14)] .

Neither a loading dose nor any supplemental oral risperidone is recommended. When a dose of PERSERIS is missed, administer the next PERSERIS injection as soon as possible.

2.2 Dosage Recommendations for Patients with Renal or Hepatic Impairment

Prior to initiating treatment with PERSERIS in patients with renal or hepatic impairment, titrate with oral risperidone up to at least 3 mg daily. Following oral titration, and based on clinical response and tolerability, the recommended dosage of PERSERIS is 90 mg once monthly [see Use in Specific Populations (8.6, 8.7) and Clinical Pharmacology (12.3)].

2.3 Dosage Recommendations for Concomitant Use with Strong CYP2D6 Inhibitors and Strong CYP3A4 Inducers

Co-administration with Strong CYP2D6 Inhibitors

Between 2 to 4 weeks prior to initiating a strong CYP2D6 inhibitor (such as fluoxetine or paroxetine), switch patients (if applicable) to the lowest PERSERIS dosage (90 mg once monthly) to adjust for the expected increase in plasma concentrations of risperidone [see Drug Interactions (7.1)] .

Co-administration with Strong CYP3A4 Inducers

With concomitant use of PERSERIS 90 mg and strong CYP3A4 inducers (such as carbamazepine), increase the PERSERIS dosage to 120 mg once monthly and consider starting additional oral risperidone therapy. In patients already receiving PERSERIS 120 mg once monthly, additional oral risperidone therapy may need to be considered.

Upon discontinuation of a strong CYP3A4 inducer in a patients receiving PERSERIS 120 mg once monthly, re-evaluate the dosage of PERSERIS or any additional oral risperidone therapy and, if necessary, decrease to adjust for the expected increase in plasma concentration of risperidone.

Upon discontinuation of a strong CYP3A4 inducer in a patient receiving PERSERIS 90 mg once monthly, continue treatment with the 90 mg dose unless clinical judgment necessitates interruption of PERSERIS treatment [see Drug Interactions (7.1)] .

2.4 Preparation and Administration Instructions

- Read the instructions for preparation and administration below and consider referring to the separate Healthcare Provider “Instructions for Use” for additional preparation and administration considerations.
- For subcutaneous injection only. Do not inject by any other route.
- Allow package to come to room temperature for at least 15 minutes prior to preparation. Prepare medication when you are ready to administer the dose.

1 CHECK CONTENTS

Each carton of PERSERIS contains (Figure 1):

- One Liquid Syringe() prefilled with the delivery system. Inspect liquid solution for foreign particles. This is the syringe you will use to inject the patient.
- One Powder Syringe() prefilled with Risperidone powder. Inspect syringe for consistency of powder color and for foreign particles.
- One sterile 18-gauge, 5/8-inch safety needle.

Figure 1

2 TAP POWDER SYRINGE

Hold the Powder Syringeupright and tap the barrel of the syringe to dislodge the packed powder (Figure 2). Note: Powder can become packed during shipping.

Figure 2

3 UNCAP LIQUID AND POWDER SYRINGES

Remove the cap from the Liquid Syringe, then remove the cap from the Powder Syringe(Figure 3).

Holding both syringes in your non-dominant hand can help with this step.

Figure 3

4 CONNECT THE SYRINGES

Place the Liquid Syringeon top of the Powder Syringe(to prevent powder spillage) and connect the syringes by twisting approximately ¾ turn (Figure 4). Do not over tighten.

Keep your fingers off the plungers during this step to avoid spillage of the medication.

Figure 4

5 MIX THE PRODUCT

Failure to fully mix the medication could result in incorrect dosage.

Premixing

- Transfer the contents of the Liquid Syringeinto the Powder Syringe.
- Gently push the Powder Syringeplunger until you feel resistance (to wet powder and avoid compacting).
- Repeat this gentle back-and-forth process for 5 cycles.

Complete mixing

- Continue mixing the syringes for an additional 55 cycles.
- This mixing can be more vigorous than when premixing.

See Figure 5for an illustration of a correct full cycle.

Figure 5

When fully mixed, the product should be a cloudy suspension that is uniform in color. It can vary from white to yellow-green in color. If you see any clear areas in the mixture, continue to mix until the distribution of the color is uniform. The product is designed to deliver risperidone 90 mg or 120 mg.

6 PREPARE INJECTION SYRINGE

Failure to aspirate the liquid from the Powder Syringemay result in incorrect dosage.

- First, transfer all contents into the Liquid Syringe(Figure 6).
- Next, perform the following actions SIMULTANEOUSLY:
  - maintain slight pressure on the Powder Syringeplunger and
  - pull back gentlyon the Liquid Syringeplunger while twisting the syringes apart.
- Finally, attach the safety needle by twisting until finger tight.
- Check that medication is uniform in color and free from foreign particles.

Figure 6

7 PREPARE THE SUBCUTANEOUS INJECTION SITE(S)

This medication is to be injected subcutaneously in the abdomen or back of the upper arm (Figure 7).

Choose an injection site with adequate subcutaneous tissue that is free of skin conditions (e.g., nodules, lesions, excessive pigment).

Do notinject into an area where the skin is irritated, reddened, bruised, infected or scarred in any way.

Clean the injection site well with an alcohol pad.

To help minimize irritation, rotate injection sites following a pattern similar to the illustration. If you want to use the same injection site, make sure it is not the same spot on the injection site you used the last time.

Figure 7

8 REMOVE EXCESS AIR FROM SYRINGE

Hold the syringe upright for several seconds to allow air bubbles to rise. Remove needle cover and slowly depress the plunger to push out the excess air from the syringe (Figure 8).

If medication is seen at the needle tip, pull back slightly on the plunger to prevent medication spillage.

Due to the viscous nature of the medication, bubbles will not rise as quickly as those in an aqueous solution.

Figure 8

9 PINCH INJECTION SITE

Pinch the skin around the injection area. Be sure to pinch enough skin to accommodate the size of the needle (Figure 9). Lift the adipose tissue from the underlying muscle to prevent accidental intramuscular injection.

Figure 9

10 INJECT THE MEDICATION

Insert needle fully into the subcutaneous tissue. Inject the medication slow and steady (Figure 10).

PERSERIS is for subcutaneous administration only. Do not inject by any other route. Actual angle of injection will depend on the amount of subcutaneous tissue.

Figure 10

11 WITHDRAW NEEDLE

Withdraw the needle at the same angle used for insertion and release pinched skin (Figure 11).

Do not rub the injection area after the injection. If there is bleeding, apply a gauze pad or bandage but use minimal pressure.

Figure 11

12 LOCK THE NEEDLE GUARD AND DISPOSE OF SYRINGE

Lock the needle guard into place by pushing it against a hard surface such as a table (Figure 12).

Figure 12

13 INSTRUCT THE PATIENT

The patient may have a lump for several weeks that will decrease in size over time (Figure 13). It is important that the patient not rub or massage the injection site and to be aware of the placement of any belts, waistbands, sleeves, cuffs or other parts of clothing.

Figure 13

3 DOSAGE FORMS AND STRENGTHS

PERSERIS (risperidone) for extended-release injectable suspension for subcutaneous use is available in strengths of 90 mg and 120 mg.

Each strength is provided as a kit which includes: one pre-filled syringe containing a white to yellow risperidone powder in a sealed pouch, one pre-filled syringe containing a colorless to yellow delivery system in a sealed pouch, and one 18-gauge, 5/8-inch needle.

4 CONTRAINDICATIONS

PERSERIS is contraindicated in patients with a known hypersensitivity to risperidone, its metabolite, paliperidone, or to any of its components. Hypersensitivity reactions, including anaphylactic reactions and angioedema, have been reported in patients treated with risperidone or paliperidone.

5 WARNINGS AND PRECAUTIONS

5.1 Increased Mortality in Elderly Patients with Dementia-Related Psychosis

Elderly patients with dementia-related psychosis treated with antipsychotic drugs are at an increased risk of death. Analyses of 17 placebo-controlled trials (modal duration of 10-weeks), largely in patients taking atypical antipsychotic drugs, revealed a risk of death in drug-treated patients between 1.6- to 1.7-times the risk of death in placebo-treated patients. Over the course of a typical 10-week controlled trial, the rate of death in drug-treated patients was about 4.5%, compared to a rate of about 2.6% in the placebo group. Although the causes of death were varied, most of the deaths appeared to be either cardiovascular (e.g., heart failure, sudden death) or infectious (e.g., pneumonia) in nature. Observational studies suggest that, similar to atypical antipsychotic drugs, treatment with conventional antipsychotic drugs may increase mortality. The extent to which the findings of increased mortality in observational studies may be attributed to the antipsychotic drug as opposed to some characteristic(s) of the patients is not clear.

PERSERIS is not approved for the treatment of patients with dementia-related psychosis [see Warnings and Precautions (5.2)] .

5.2 Cerebrovascular Adverse Reactions, Including Stroke, in Elderly Patients with Dementia-Related Psychosis

Cerebrovascular adverse reactions (e.g., stroke, transient ischemic attack), including fatalities, were reported in patients (mean age 85-years; range 73 to 97) in trials of oral risperidone in elderly patients with dementia-related psychosis. In placebo-controlled trials, there was a significantly higher incidence of cerebrovascular adverse reactions in patients treated with oral risperidone compared to patients treated with placebo. PERSERIS is not approved for the treatment of patients with dementia-related psychosis [see Warnings and Precautions (5.1)] .

5.3 Neuroleptic Malignant Syndrome (NMS)

NMS, a potentially fatal symptom complex, has been reported in association with antipsychotic drugs. Clinical manifestations of NMS are hyperpyrexia, muscle rigidity, altered mental status including delirium, and autonomic instability (irregular pulse or blood pressure, tachycardia, diaphoresis, and cardiac dysrhythmia). Additional signs may include elevated creatine phosphokinase, myoglobinuria (rhabdomyolysis), and acute renal failure.

If NMS is suspected, immediately discontinue PERSERIS and provide symptomatic treatment and monitoring.

5.4 Tardive Dyskinesia

Tardive dyskinesia, a syndrome consisting of potentially irreversible, involuntary, dyskinetic movements, may develop in patients treated with antipsychotic drugs. Although the prevalence of the syndrome appears to be highest among the elderly, especially elderly women, it is impossible to rely upon prevalence estimates to predict which patients will develop the syndrome. Whether antipsychotic drug products differ in their potential to cause tardive dyskinesia is unknown.

The risk of developing tardive dyskinesia and the likelihood that it will become irreversible are believed to increase with the duration of treatment and the total cumulative dose. The syndrome can develop after relatively brief treatment periods, even at low doses. It may also occur after discontinuation of treatment.

Tardive dyskinesia may remit, partially or completely, if antipsychotic treatment is discontinued. Antipsychotic treatment, itself, however, may suppress (or partially suppress) the signs and symptoms of the syndrome and thereby may possibly mask the underlying process. The effect that symptomatic suppression has upon the long-term course of the syndrome is unknown.

Given these considerations, PERSERIS should be prescribed in a manner that is most likely to minimize the occurrence of tardive dyskinesia. Chronic antipsychotic treatment should generally be reserved for patients: 1) who suffer from a chronic illness that is known to respond to antipsychotic drugs, and (2) for whom alternative, equally effective, but potentially less harmful treatments are not available or appropriate. In patients who do require chronic treatment, use the lowest dose and the shortest duration of treatment producing a satisfactory clinical response. Periodically reassess the need for continued treatment.

If signs and symptoms of tardive dyskinesia appear in a patient treated with PERSERIS, drug discontinuation should be considered. However, some patients may require treatment with PERSERIS despite the presence of the syndrome.

5.5 Metabolic Changes

Atypical antipsychotic drugs have been associated with metabolic changes that may increase cardiovascular/cerebrovascular risk. These metabolic changes include hyperglycemia, dyslipidemia, and body weight gain. While all of the drugs in the class have been shown to produce some metabolic changes, each drug has its own specific risk profile.

Hyperglycemia and Diabetes Mellitus

Hyperglycemia and diabetes mellitus, in some cases extreme and associated with ketoacidosis or hyperosmolar coma or death, have been reported in patients treated with atypical antipsychotics including risperidone. Assessment of the relationship between atypical antipsychotic use and glucose abnormalities is complicated by the possibility of an increased background risk of diabetes mellitus in patients with schizophrenia and the increasing incidence of diabetes mellitus in the general population. Given these confounders, the relationship between atypical antipsychotic use and hyperglycemia-related adverse events is not completely understood. However, epidemiological studies suggest an increased risk of hyperglycemia-related events in patients treated with the atypical antipsychotics. Precise risk estimates for hyperglycemia-related adverse events in patients treated with atypical antipsychotics are not available.

Patients with an established diagnosis of diabetes mellitus who are started on atypical antipsychotics, including PERSERIS, should be monitored regularly for worsening of glucose control. Patients with risk factors for diabetes mellitus (e.g., obesity, family history of diabetes) who are starting treatment with atypical antipsychotics, including PERSERIS, should undergo fasting blood glucose testing at the beginning of treatment and periodically during treatment. Any patient treated with atypical antipsychotics, including PERSERIS, should be monitored for symptoms of hyperglycemia including polydipsia, polyuria, polyphagia, and weakness. Patients who develop symptoms of hyperglycemia during treatment with atypical antipsychotics, including PERSERIS, should undergo fasting blood glucose testing. In some cases, hyperglycemia has resolved when the atypical antipsychotic, including risperidone, was discontinued; however, some patients required continuation of anti-diabetic treatment despite discontinuation of risperidone.

Data from an 8-week double-blind, placebo-controlled study with PERSERIS in adult patients with schizophrenia are presented in Table 1.

Table 1 Changes in Fasting Glucose from Baseline to End of Study (EOS) and Postbaseline Abnormal Values of Glucose > 126 mg/dL in an 8-Week Double-Blind, Placebo-Controlled Study in Adult Patients with Schizophrenia
 | PERSERIS 90 mg | PERSERIS 120 mg | Placebo
 | n = 98 | n = 106 | n = 96
Serum Glucose, mg/dL, mean†
Mean Change from Baseline to EOS | 5.7 | 6.3 | -0.9
Glucose, > 126 mg/dL
Proportion of Patients with Postbaseline Abnormal Values‡ | 12/104 (11.5%) | 14/111 (12.6%) | 8/109 (7.3%)
†The “n”s in the Serum Glucose mean row are the number of patients with data at baseline and EOS visits.
‡Data shown as number of patients with at least one postbaseline value as denominator and number of patients satisfying the predefined criterion as numerator.

Similar changes from baseline in serum glucose were observed in patients receiving PERSERIS during an open-label, 12-month long-term safety study. Additionally, the mean HbA1cincreased from 5.6 to 5.7% over the 12-months.

Dyslipidemia

Undesirable alterations in lipids have been observed in patients treated with atypical antipsychotics. Before or soon after initiation of antipsychotic medications, obtain a fasting lipid profile at baseline and monitor periodically during treatment.

Data from an 8-week double-blind, placebo-controlled study with PERSERIS in adult patients with schizophrenia are presented in Table 2.

Table 2 Changes in Cholesterol from Baseline to End of Study (EOS) and Postbaseline Abnormal Values of Cholesterol ≥ 300 mg/dL in an 8-Week Double-Blind, Placebo-Controlled Study in Adult Patients with Schizophrenia
 | PERSERIS 90 mg | PERSERIS 120 mg | Placebo
Cholesterol, mg/dL, mean† | n = 98 | n = 106 | n = 96
Mean Change from Baseline to EOS | -0.5 | -0.5 | 1.1
Cholesterol, ≥ 300 mg/dL
Proportion of Patients with Postbaseline Abnormal Values‡ | 2/104 (1.9%) | 2/111 (1.8%) | 2/109 (1.8%)
†The “n”s in the Cholesterol mean row are the number of patients with data at baseline and EOS visits.
‡Data shown as number of patients with at least one postbaseline value as denominator and number of patients satisfying the predefined criterion as numerator.

Weight Gain

Weight gain has been observed with atypical antipsychotic use. Clinical monitoring of weight is recommended.

Data from an 8-week double-blind, placebo-controlled study with PERSERIS in adult patients with schizophrenia are presented in Table 3.

Table 3 Changes in Body Weight from Baseline to End of Study (EOS) and ≥ 7% Increase from Baseline in an 8-Week Double-Blind, Placebo-Controlled Study in Adult Patients with Schizophrenia
 | PERSERIS 90 mg | PERSERIS 120 mg | Placebo
Weight† | n = 105 | n = 112 | n = 107
Mean Change from Baseline to EOS, kg | 4.4 | 5.3 | 2.6
Weight Gain
≥ 7% Increase from Baseline‡ | 35/107 (32.7%) | 48/114 (42.1%) | 20/111 (18.0%)
†The “n”s in the Weight Change mean row are the number of patients with data at baseline and end of study visits.
‡ Data shown as number of patients with at least one postbaseline value as denominator and number of patients satisfying the predefined criterion as numerator.

In an open-label, 12-month long-term safety study, for all patients receiving PERSERIS, mean weight increased approximately 2 kg from baseline to Day 85, then remained stable for the remainder of the study.

5.6 Hyperprolactinemia

As with other drugs that antagonize dopamine D2receptors, risperidone elevates prolactin levels and the elevation persists during chronic administration. Risperidone is associated with higher levels of prolactin elevation than other antipsychotic agents.

Hyperprolactinemia may suppress hypothalamic GnRH, resulting in reduced pituitary gonadotropin secretion. This, in turn, may inhibit reproductive function by impairing gonadal steroidogenesis in both female and male patients [see Use in Specific Populations (8.3)] . Galactorrhea, amenorrhea, gynecomastia, and impotence have been reported in patients receiving prolactin-elevating compounds. Long-standing hyperprolactinemia when associated with hypogonadism may lead to decreased bone density in both female and male patients.

Tissue culture experiments indicate that approximately one-third of human breast cancers are prolactin dependent in vitro, a factor of potential importance if the prescription of these drugs is contemplated in a patient with previously detected breast cancer. An increase in pituitary gland, mammary gland, and pancreatic islet cell neoplasia (mammary adenocarcinomas, pituitary and pancreatic adenomas) was observed in the risperidone carcinogenicity studies conducted in mice and rats [see Nonclinical Toxicology (13.1)] . Published epidemiologic studies have shown inconsistent results when exploring the potential association between hyperprolactinemia and breast cancer.

5.7 Orthostatic Hypotension and Syncope

Risperidone may induce orthostatic hypotension associated with dizziness, tachycardia, and in some patients, syncope, particularly at the time of initiating treatment, re-initiating treatment, or increasing the dose, probably reflecting its alpha-adrenergic antagonistic properties.

PERSERIS should be used with particular caution in (1) patients with known cardiovascular disease (history of myocardial infarction or ischemia, heart failure, or conduction abnormalities), cerebrovascular disease, and conditions which would predispose patients to hypotension, e.g., dehydration and hypovolemia, and (2) in the elderly and patients with renal or hepatic impairment. Monitoring of orthostatic vital signs should be considered in all such patients, and a dose reduction should be considered if hypotension occurs. Clinically significant hypotension has been observed with concomitant use of oral risperidone and antihypertensive medication.

5.8 Falls

Somnolence, postural hypotension, motor instability, and sensory instability have been reported with the use of antipsychotics, including PERSERIS, which may lead to falls and, consequently, fractures or other fall-related injuries. For patients, particularly the elderly, with diseases, conditions, or medications that could exacerbate these effects, assess the risk of falls when initiating antipsychotic treatment and recurrently for patients on long-term antipsychotic therapy.

5.9 Leukopenia, Neutropenia, and Agranulocytosis

In clinical trial and/or postmarketing experience, events of leukopenia/neutropenia have been reported temporally related to antipsychotic agents, including risperidone. Agranulocytosis has also been reported.

Possible risk factors for leukopenia and neutropenia include pre-existing low white blood cell count (WBC) or absolute neutrophil count (ANC) and a history of drug-induced leukopenia or neutropenia. In patients with a pre-existing history of a clinically significant low WBC or ANC or a history of drug-induced leukopenia or neutropenia, perform a complete blood count (CBC) frequently during the first few months of therapy. In such patients, consider discontinuation of PERSERIS at the first sign of a clinically significant decline in WBC in the absence of other causative factors.

Monitor patients with clinically significant neutropenia for fever or other symptoms or signs of infection and treat promptly if such symptoms or signs occur. Discontinue PERSERIS in patients with absolute neutrophil count <1000/mm^3and follow their WBC until recovery.

5.10 Potential for Cognitive and Motor Impairment

PERSERIS, like other antipsychotics, may cause somnolence and has the potential to impair judgement, thinking, and motor skills.

In an 8-week, double-blind, placebo-controlled study, somnolence/sedation was reported by 7.0% and 7.7% of patients treated with PERSERIS 90 mg and 120 mg, respectively.

Patients should be cautioned about operating hazardous machinery, including motor vehicles, until they are reasonably certain that treatment with PERSERIS does not affect them adversely.

5.11 Seizures

Seizures were observed during premarketing studies of risperidone in adult patients with schizophrenia. PERSERIS should be used cautiously in patients with a history of seizures or other conditions that potentially lower the seizure threshold.

5.12 Dysphagia

Esophageal dysmotility and aspiration have been associated with antipsychotic drug use. Aspiration pneumonia is a common cause of morbidity and mortality in patients with advanced Alzheimer's dementia. Antipsychotic drugs, including PERSERIS, should be used cautiously in patients at risk for aspiration [see Warnings and Precautions (5.1)] .

5.13 Priapism

Priapism has been reported during postmarketing surveillance for other risperidone products. Severe priapism may require surgical intervention.

5.14 Body Temperature Regulation

Atypical antipsychotics may disrupt the body's ability to reduce core body temperature. Both hyperthermia and hypothermia have been reported in association with oral risperidone use. Strenuous exercise, exposure to extreme heat, dehydration, and anticholinergic medications may contribute to an elevation in core body temperature; use PERSERIS with caution in patients who may experience these conditions.

6 ADVERSE REACTIONS

The following are discussed in more detail in previous sections of the labeling:

- Increased Mortality in Elderly Patients with Dementia-Related Psychosis [see Boxed Warningand Warnings and Precautions (5.1)]
- Cerebrovascular Adverse Reactions, Including Stroke, in Elderly Patients with Dementia-Related Psychosis [see Warnings and Precautions (5.2)]
- Neuroleptic Malignant Syndrome (NMS) [see Warnings and Precautions (5.3)]
- Tardive Dyskinesia [see Warnings and Precautions (5.4)]
- Metabolic Changes [see Warnings and Precautions (5.5)]
- Hyperprolactinemia [see Warnings and Precautions (5.6)]
- Orthostatic Hypotension and Syncope [see Warnings and Precautions (5.7)]
- Falls [see Warnings and Precautions (5.8)]
- Leukopenia, Neutropenia and Agranulocytosis [see Warnings and Precautions (5.9)]
- Potential for Cognitive and Motor Impairment [see Warnings and Precautions (5.10)]
- Seizures [see Warnings and Precautions (5.11)]
- Dysphagia [see Warnings and Precautions (5.12)]
- Priapism [see Warnings and Precautions (5.13)]
- Body Temperature Regulation [see Warnings and Precautions (5.14)]

6.1 Clinical Trials Experience

Because clinical trials are conducted under widely varying conditions, adverse reaction rates observed in the clinical trials of a drug cannot be directly compared to rates in the clinical trials of another drug and may not reflect the rates observed in practice.

The safety of PERSERIS was evaluated in a total of 837 adult patients with schizophrenia who received at least 1 dose of PERSERIS during the clinical development program. A total of 322 patients were exposed to PERSERIS for at least 6 months, of which 234 patients were exposed to PERSERIS for at least 12 months; 281 and 176 of these, respectively, received the 120 mg dose.

Adverse drug reactions in adult patients with schizophrenia (≥ 5% in any PERSERIS-treated group and greater than placebo) during the 8-week double-blind, placebo-controlled study) were weight increased, constipation, sedation/somnolence, pain in extremity, back pain, akathisia, anxiety, and musculoskeletal pain. In addition, the frequency of reported injection site reactions was similar across treatment groups with both PERSERIS and placebo; the most common (≥ 5%) of which were injection site pain, and erythema. The systemic safety profile for PERSERIS was consistent with the known safety profile of oral risperidone.

Commonly-Observed Adverse Drug Reactions in Double-Blind, Placebo-Controlled Clinical Studies – Schizophrenia

Adverse Reactions with an incidence of 2% or more and greater than placebo are shown in Table 4.

Table 4 Adverse Drug Reactions in 2% or More of PERSERIS-Treated Patients (and Greater than Placebo) in an 8-Week Double-Blind, Placebo-Controlled Study
System Organ Class Preferred Term | PERSERIS 90 mg (n = 115) | PERSERIS 120 mg (n = 117) | Placebo (n = 118)
 | Percentage of Patients Reporting ADR
Gastrointestinal disorders
Constipation | 7.0 | 7.7 | 5.1
Abdominal discomfort | 2.6 | 2.6 | 1.7
Dry mouth | 1.7 | 2.6 | 1.7
Investigations
Weight increased | 13.0 | 12.8 | 3.4
Metabolism and nutrition disorders
Increased appetite | 1.7 | 3.4 | 1.7
Musculoskeletal and connective tissue disorders
Back pain | 3.5 | 6.8 | 4.2
Pain in extremity | 0.9 | 7.7 | 5.1
Musculoskeletal pain | 5.2 | 5.1 | 2.5
Musculoskeletal stiffness | 2.6 | 0.9 | 1.7
Muscle spasms | 0 | 2.6 | 0
Nervous system disorders
Sedation* | 7.0 | 7.7 | 0
Akathisia | 2.6 | 6.8 | 4.2
Extrapyramidal disorder | 4.3 | 1.7 | 0.8
Psychiatric disorders
Anxiety | 2.6 | 6.8 | 5.1
* Sedation includes sedation and somnolence

Other Adverse Drug Reactions Observed During the Clinical Trial Evaluation of PERSERIS

The following list does not include reactions: 1) already listed in previous tables or elsewhere in labeling, 2) which are part of the disease state, 3) for which a drug cause was remote, 4) which were so general as to be uninformative, or 5) which were not considered to have significant clinical implications.

Blood and Lymphatic System Disorders:neutropenia

Ear and Labyrinth Disorders:vertigo

Endocrine Disorders:hyperprolactinemia

Eye Disorders:blepharospasm

Gastrointestinal Disorders:nausea, dyspepsia, vomiting, diarrhea, abdominal pain upper, salivary hypersecretion, hypoesthesia oral, tongue movement disturbance

General Disorders and Administration Site Conditions:injection site reaction (including injection site pain, induration, pruritus, bruising, erythema, inflammation, swelling and irritation) fatigue, edema peripheral, asthenia, chest discomfort

Investigations:blood prolactin increased, blood glucose increased, glycosylated hemoglobin increased, electrocardiogram abnormal, electrocardiogram QT prolonged, blood creatine phosphokinase increased

Metabolism and Nutrition Disorders:diabetes mellitus, decreased appetite

Musculoskeletal, Connective Tissue, and Bone Disorders:arthralgia, muscle twitching, joint stiffness, trismus

Nervous System Disorders:headache, dizziness, tremor, drooling, dyskinesia, lethargy, dystonia, hypoesthesia, oromandibular dystonia, tardive dyskinesia, cogwheel rigidity, dysarthria, balance disorder, parkinsonian rest tremor, parkinsonism, slow speech

Psychiatric Disorders:insomnia, libido decreased, bruxism, restlessness, anorgasmia, loss of libido

Reproductive System and Breast Disorders:erectile dysfunction, galactorrhea, breast tenderness, breast pain, amenorrhea, breast engorgement, ejaculation delayed, ejaculation disorder, gynecomastia, hypomenorrhea, breast discharge, breast enlargement, ejaculation failure, menstruation delayed, menstruation irregular, polymenorrhea

Skin and Subcutaneous Tissue Disorders:night sweats

Vascular Disorders:hypertension, hypotension, orthostatic hypotension

Other Adverse Reactions Observed During the Clinical Trial Evaluations of Oral Risperidone

The following is a list of additional ADRs that have been reported during the clinical trial evaluation of oral risperidone, regardless of frequency of occurrence:

Blood and Lymphatic System Disorders:anemia, granulocytopenia

Cardiac Disorders:tachycardia, sinus bradycardia, sinus tachycardia, atrioventricular block first degree, bundle branch block left, bundle branch block right, atrioventricular block

Ear and Labyrinth Disorders:ear pain, tinnitus

Eye Disorders:vision blurred, oculogyration, ocular hyperemia, eye discharge, conjunctivitis, eye rolling, eyelid edema, eye swelling, eyelid margin crusting, dry eye, lacrimation increased, photophobia, glaucoma, visual acuity reduced

Gastrointestinal Disorders:dysphagia, fecaloma, fecal incontinence, gastritis, lip swelling, cheilitis, aptyalism

General Disorders:thirst, gait disturbance, chest pain, influenza-like illness, pitting edema, edema, chills, sluggishness, malaise, face edema, discomfort, generalized edema, drug withdrawal syndrome, peripheral coldness, feeling abnormal

Immune System Disorders:drug hypersensitivity

Infections and Infestations:nasopharyngitis, upper respiratory tract infection, sinusitis, urinary tract infection, pneumonia, influenza, ear infection, viral infection, pharyngitis, tonsillitis, bronchitis, eye infection, localized infection, cystitis, cellulitis, otitis media, onychomycosis, acarodermatitis, bronchopneumonia, respiratory tract infection, tracheobronchitis, otitis media chronic

Investigations:body temperature increased, alanine aminotransferase increased, heart rate increased, eosinophil count increased, white blood cell count decreased, hemoglobin decreased, blood creatine phosphokinase increased, hematocrit decreased, body temperature decreased, blood pressure decreased, transaminases increased

Metabolism and Nutrition Disorders:polydipsia, anorexia

Musculoskeletal, Connective Tissue, and Bone Disorders:joint swelling, musculoskeletal chest pain, posture abnormal, myalgia, neck pain, muscular weakness, muscle rigidity, muscle contracture, rhabdomyolysis

Nervous System Disorders:dizziness postural, disturbance in attention, unresponsive to stimuli, depressed level of consciousness, movement disorder, hypokinesia, bradykinesia, transient ischemic attack, coordination abnormal, cerebrovascular accident, masked facies, speech disorder, syncope, loss of consciousness, muscle contractions involuntary, Parkinson's disease, tongue paralysis, akinesia, cerebral ischemia, cerebrovascular disorder, neuroleptic malignant syndrome, diabetic coma, head titubation

Psychiatric Disorders:agitation, blunted affect, confusional state, middle insomnia, nervousness, sleep disorder, listlessness

Renal and Urinary Disorders:enuresis, dysuria, pollakiuria, urinary incontinence

Reproductive System and Breast Disorders:vaginal discharge, menstrual disorder, retrograde ejaculation, sexual dysfunction

Respiratory, Thoracic, and Mediastinal Disorders:nasal congestion, dyspnea, epistaxis, wheezing, pneumonia aspiration, sinus congestion, dysphonia, productive cough, pulmonary congestion, respiratory tract congestion, rales, respiratory disorder, hyperventilation, nasal edema

Skin and Subcutaneous Tissue Disorders:rash, dry skin, erythema, skin discoloration, skin lesion, pruritus, skin disorder, rash erythematous, rash papular, acne, hyperkeratosis, seborrheic dermatitis, rash generalized, rash maculopapular

Vascular Disorders:flushing

Discontinuations Due to Adverse Drug Reactions (ADRs)

There was no single adverse reaction leading to discontinuation that occurred at a rate of ≥ 2% in PERSERIS-treated patients and greater than placebo.

Dose Dependency of Adverse Drug Reactions in Clinical Trials

Changes in Body Weight

Data from the double-blind placebo-controlled study indicated there was a dose-dependent increase in mean changes in weight from baseline to postdose assessments in the PERSERIS 90 mg and 120 mg groups compared with the placebo group [see Warnings and Precautions (5.5), Adverse Reactions (6.1, Table 4)] .

Increased Prolactin

In the 8-week double-blind, placebo-controlled study, there was a typical increase in mean prolactin levels in fasting blood samples from baseline to the EOS assessments in both the PERSERIS 90 mg and 120 mg groups, while mean prolactin for the placebo group remained stable during the study. Changes in mean prolactin were dose-dependent and more pronounced in female patients than male patients.

Extrapyramidal Symptoms (EPS)

Several methods were used to measure EPS, including: (1) the Barnes Akathisia Rating Scale (BARS) global clinical rating score which evaluates akathisia, (2) the Abnormal Involuntary Movement Scale (AIMS) scores which evaluates dyskinesia, (3) the Simpson-Angus Scale (SAS) global score which broadly evaluates parkinsonism, and (4) the incidence of spontaneous reports of EPS-related adverse reactions.

In the 8-week double-blind, placebo-controlled study, the mean changes from baseline in BARS, AIMS, and SAS total scores were comparable between PERSERIS- and placebo-treated patients. At all postbaseline assessments, mean changes from baseline were between -0.1 and 0.2 (inclusive) for the BARS, between 0 and 0.2 (inclusive) for the AIMS and between -0.1 and 0.2 (inclusive) for the SAS.

The rates of ADRs associated with EPS were similar across treatment groups, including placebo. There was a higher incidence of akathisia in the PERSERIS 120 mg (6.8%) group compared with the PERSERIS 90 mg (2.6%) and placebo group (4.2%); reports of extrapyramidal disorders were higher in the PERSERIS 90 mg group (4.3%) compared with the PERSERIS 120 mg (1.7%) and placebo group (0.8%). In contrast, there was a higher incidence of dystonia in the placebo group (2.5%) compared with the PERSERIS groups (0 and 0.9%, respectively).

Dystonia

Symptoms of dystonia, prolonged abnormal contractions of muscle groups, may occur in susceptible individuals during the first few days of treatment. Dystonic symptoms include: spasm of the neck muscles, sometimes progressing to tightness of the throat, swallowing difficulty, difficulty breathing, and/or protrusion of the tongue. Although these symptoms can occur at low doses, they occur more frequently and with greater severity with high potency and at higher doses of first generation antipsychotic drugs. An elevated risk of acute dystonia has been observed in males and younger age groups.

Changes in ECG

In the 8-week double-blind, placebo-controlled study, there were no clinically relevant differences in mean changes from baseline to EOS in ECG parameters, including QTcF (Fridericia's corrected QT interval), QRS and PR intervals, and heart rate, in patients in either PERSERIS treatment group (90 mg and 120 mg) compared with placebo. Similarly, in the 12-month, long-term safety study, there were no clinically relevant changes in mean ECG interval values from baseline to postdose assessments.

Pain Assessment and Local Injection Site Reactions

Local injection site pain was assessed using patient-reported VAS scales (0 = no pain to 100 = unbearably painful). In the 8-week, double-blind placebo-controlled study, the mean patient-reported injection site pain VAS scores were similar for all treatment groups following both injections. Pain scores decreased from a mean of 27 (VAS score) 1 minute after the first dose to a range of 3 to 7 (VAS score) 30 to 60 minutes postdose. In the 12-month, long-term safety study, the 1-minute postdose injection site pain VAS scores were highest on Day 1 (mean of 25) and decreased over time with subsequent injections (14 to 16 following last injection).

The local injection site was assessed by appropriately trained personnel. Throughout the clinical development program, the maximum reported intensity at any time point for each injection site assessment (pain, tenderness, inflammation/swelling and erythema) was none or mild for most patients receiving PERSERIS.

Most patients (≥ 79%) reported no tenderness and most who had tenderness reported mild severity. Less than 1% of patients had moderate tenderness at any time point and 1 patient at Injections 1, 2, and 5 had severe tenderness. At each time point, most patients (≥ 75%) reported no pain on injection. Of patients who did have pain on injection, almost all of these were mild at each time point; only 1 or 2 patients at Injections 1, 2, 7, and 12 had moderate pain on injection. At least 92% of patients reported no erythema on each injection. All reports of erythema were of mild severity except for 2 cases of moderate erythema on Injection 1. Inflammation/swelling had a similar profile, with at least 88% of patients reporting no inflammation/swelling and only mild symptoms except for 1 case of moderate severity on Injection 1.

6.2 Postmarketing Experience

The following adverse reactions have been identified during post approval use of oral risperidone. Because these reactions are reported voluntarily from a population of uncertain size, it is not always possible to reliably estimate their frequency or establish a causal relationship to drug exposure. These adverse reactions include: alopecia, anaphylactic reaction, angioedema, atrial fibrillation, cardiopulmonary arrest, catatonia, diabetic ketoacidosis in patients with impaired glucose metabolism, dysgeusia, hypoglycemia, hypothermia, ileus, inappropriate antidiuretic hormone secretion, intestinal obstruction, jaundice, mania, pancreatitis, pituitary adenoma, precocious puberty, pulmonary embolism, QT prolongation, sleep apnea syndrome, somnambulism, Stevens-Johnson syndrome and toxic epidermal necrolysis (SJS/TEN), sudden death, thrombocytopenia, thrombotic thrombocytopenic purpura, urinary retention, and water intoxication.

Postmarketing cases of extrapyramidal symptoms (dystonia and dyskinesia) have been reported in patients concomitantly taking methylphenidate and risperidone when there was an increase or decrease in dosage, initiation, or discontinuation of either or both medications.

7 DRUG INTERACTIONS

The interactions of PERSERIS with co-administration of other drugs have not been studied. The drug interaction data provided in this section is based on studies with oral risperidone.

7.1 Drugs Having Clinically Important Interactions with PERSERIS

Table 5includes clinically significant drug interactions with PERSERIS.

Table 5 Clinically Important Drug Interactions with PERSERIS
Strong CYP2D6 Inhibitors
Clinical Impact: | Concomitant use of PERSERIS with strong CYP2D6 inhibitors may increase the plasma exposure of risperidone and lower the plasma exposure of a major active metabolite, 9-hydroxyrisperidone [see Clinical Pharmacology (12.3)] .
Intervention: | When initiation of strong CYP2D6 inhibitors is considered, patients may be placed on the lowest dose (90 mg) of PERSERIS between 2 to 4 weeks before the planned start of strong CYP2D6 inhibitors to adjust for the expected increase in plasma concentrations of risperidone. When strong CYP2D6 inhibitors is initiated in patients receiving PERSERIS 90 mg, it is recommended to continue treatment with 90 mg unless clinical judgment necessitates interruption of PERSERIS treatment. The effects of discontinuation of strong CYP2D6 inhibitors on the pharmacokinetics of risperidone and 9-hydroxyrisperidone have not been studied [see Clinical Pharmacology (12.3)] .
Strong CYP3A4 Inducers
Clinical Impact: | Concomitant use of PERSERIS and a strong CYP3A4 inducer may cause decreases in the combined plasma concentrations of risperidone and 9-hydroxyrisperidone which could lead to decreased efficacy of PERSERIS [see Clinical Pharmacology (12.3)] .
Intervention: | Changes in efficacy and safety should be carefully monitored with any dose adjustment of PERSERIS. At the initiation of therapy with a strong CYP3A4 inducer, patients should be closely monitored during the first 4 to 8 weeks. In patients receiving PERSERIS 90 mg, consider increasing the dose to 120 mg. In patients receiving PERSERIS 120 mg, additional oral risperidone therapy may need to be considered. On discontinuation of a strong CYP3A4 inducer, the dosage of PERSERIS or any additional oral risperidone therapy should be re-evaluated and, if necessary, decreased to adjust for the expected increase in plasma concentration of risperidone and 9-hydroxyrisperidone. For patients treated with PERSERIS 90 mg and discontinuing from a strong CYP3A4 inducer, it is recommended to continue treatment with the 90 mg dose unless clinical judgment necessitates interruption of PERSERIS treatment [see Dosage and Administration (2.3)] .
Centrally-Acting Drugs and Alcohol
Clinical Impact: | Due to additive pharmacologic effects, the concomitant use of centrally-acting drugs, including alcohol, may increase nervous system disorders.
Intervention: | Caution should be used when PERSERIS is administered in combination with other centrally-acting drugs or alcohol.
Hypotensive Agents
Clinical Impact: | Because of its potential for inducing hypotension, PERSERIS may enhance the hypotensive effects of other therapeutic agents with this potential.
Intervention: | Caution should be used when PERSERIS is administered in combination with other therapeutic agents with hypotensive effects.
Dopamine Agonists
Clinical Impact: | Agents with central antidopaminergic activity such as PERSERIS may antagonize the pharmacologic effects of dopamine agonists.
Intervention: | Caution should be used when PERSERIS is administered in combination with levodopa and dopamine agonists.
Methylphenidate
Clinical Impact: | Concomitant use with methylphenidate, when there is change in dosage of either medication, may increase the risk of extrapyramidal symptoms (EPS) [see Adverse Reactions (6.2)] .
Intervention: | Monitor for symptoms of EPS with concomitant use of PERSERIS and methylphenidate.

7.2 Drugs Having No Clinically Important Interactions with PERSERIS

Based on pharmacokinetic studies with oral risperidone, no dosage adjustment of PERSERIS is required when administered concomitantly with amitriptyline, cimetidine, ranitidine, clozapine, topiramate and moderate CYP3A4 inhibitors (erythromycin). Additionally, no dosage adjustment is necessary for lithium, valproate, topiramate, digoxin and CYP2D6 substrates (donepezil and galantamine) when co-administered with PERSERIS [see Clinical Pharmacology (12.3)] .

8 USE IN SPECIFIC POPULATIONS

8.1 Pregnancy

Pregnancy Exposure Registry

There is a pregnancy exposure registry that monitors pregnancy outcomes in women exposed to atypical antipsychotics, including PERSERIS, during pregnancy. Healthcare providers are encouraged to register patients by contacting the National Pregnancy Registry for Atypical Antipsychotics at 1-866-961-2388 or online at http://womensmentalhealth.org/clinical-and-research-programs/pregnancyregistry/.

Risk Summary

Neonates exposed to antipsychotic drugs during the third trimester of pregnancy are at risk for extrapyramidal and/or withdrawal symptoms following delivery (see Clinical Considerations) . Overall available data from published epidemiologic studies of pregnant women exposed to risperidone have not established a drug-associated risk of major birth defects, miscarriage, or adverse maternal or fetal outcomes (see Data). There are risks to the mother associated with untreated schizophrenia and with exposure to antipsychotics, including PERSERIS, during pregnancy (see Clinical Considerations) .

Oral administration of risperidone to pregnant mice caused cleft palate at doses 3 to 4 times the oral maximum recommended human dose (MRHD) of 16 mg/day with maternal toxicity observed at 4 times the MRHD based on mg/m^2body surface area. Risperidone was not teratogenic in rats or rabbits at doses up to 6 times the oral MRHD based on mg/m^2body surface area. Increased stillbirths and decreased birth weight occurred after oral risperidone administration to pregnant rats at 1.5 times the oral MRHD based on mg/m^2body surface area. Learning was impaired in offspring of rats when the dams were dosed at 0.6 times the oral MRHD and offspring mortality increased at doses 0.1 to 3 times the oral MRHD based on mg/m^2body surface area.

Subcutaneous administration of the delivery system to pregnant rats and rabbits during the period of organogenesis caused developmental toxicity that included post-implantation loss, decreased number of live fetuses, decreased fetal weight and fetal malformations (external, skeletal, and visceral), at doses that are 52 (rat) and 43 (rabbit) times the delivery system amount present in 120 mg risperidone subcutaneous injectable suspension based on mg/m^2body surface area. These effects could be attributed to N-methyl-2-pyrrolidone (NMP) an excipient in the delivery system based on information in the published literature (see Data) . Subcutaneous administration of the delivery system to pregnant and lactating rats had no effect on embryofetal and postnatal development at doses up to 17 times the delivery system amount present in 120 mg risperidone subcutaneous injectable suspension based on mg/m^2body surface area.

The estimated background risks of major birth defects and miscarriage for the indicated population is unknown. All pregnancies have a background risk of birth defect, loss, or other adverse outcomes. In the U.S. general population, the estimated background risk of major birth defects and miscarriage in clinically recognized pregnancies is 2 to 4% and 15 to 20%, respectively.

Clinical Considerations

Disease-associated maternal and/or embryo/fetal risk

There is a risk to the mother from untreated schizophrenia, including increased risk of relapse, hospitalization, and suicide. Schizophrenia is associated with increased adverse perinatal outcomes, including preterm birth. It is not known if this is a direct result of the illness or other comorbid factors.

Fetal/neonatal adverse reactions

Extrapyramidal and/or withdrawal symptoms, including agitation, hypertonia, hypotonia, tremor, somnolence, respiratory distress, and feeding disorder have been reported in neonates who were exposed to antipsychotic drugs, including risperidone, during the third trimester of pregnancy. These symptoms have varied in severity. Monitor neonates for extrapyramidal and/or withdrawal symptoms and manage symptoms appropriately. Some neonates recovered within hours or days without specific treatment; others required prolonged hospitalization.

Data

Human Data

Published data from observational studies, birth registries, and case reports on the use of atypical antipsychotics during pregnancy do not report a clear association with antipsychotics and major birth defects. A prospective observational study including 6 women treated with risperidone demonstrated placental passage of risperidone. A retrospective cohort study from a Medicaid database of 9258 women exposed to antipsychotics during pregnancy did not indicate an overall increased risk for major birth defects. There was a small increase in the risk of major birth defects (RR = 1.26, 95% CI 1.02 to 1.56) and of cardiac malformations (RR = 1.26, 95% CI 0.88 to 1.81) in a subgroup of 1566 women exposed to risperidone during the first trimester of pregnancy; however, there is no mechanism of action to explain the difference in malformation rates.

Animal data

No developmental toxicity studies were conducted with subcutaneous risperidone suspension.

Oral administration of risperidone to pregnant mice during organogenesis caused cleft palate at 10 mg/kg/day which is 3 times the oral MRHD of 16 mg/day based on mg/m^2body surface area; maternal toxicity occurred at 4 times the oral MRHD. Risperidone was not teratogenic when administered orally to rats at 0.6 to 10 mg/kg/day and rabbits at 0.3 to 5 mg/kg/day, which are up to 6 times the oral MRHD of 16 mg/day risperidone based on mg/m^2body surface area. Learning was impaired in offspring of rats dosed orally throughout pregnancy at 1 mg/kg/day which is 0.6 times the oral MRHD and neuronal cell death increased in fetal brains of offspring of rats dosed during pregnancy at 1 and 2 mg/kg/day which are 0.6 and 1.2 times the oral MRHD based on mg/m^2body surface area; postnatal development and growth of the offspring were also delayed.

Rat offspring mortality increased during the first 4 days of lactation when pregnant rats were dosed throughout gestation at 0.16 to 5 mg/kg/day which are 0.1 to 3 times the oral MRHD of 16 mg/day based on mg/m^2body surface area. It is not known whether these deaths were due to a direct effect on the fetuses or pups or to effects on the dams; a no-effect dose could not be determined. The rate of stillbirths was increased at 2.5 mg/kg or 1.5 times the oral MRHD based on mg/m^2body surface area. In a rat cross-fostering study the number of live offspring was decreased, the number of stillbirths increased, and the birth weight was decreased in offspring of drug-treated pregnant rats. In addition, the number of deaths increased by Day 1 among offspring of drug-treated pregnant rats, regardless of whether or not the offspring were cross-fostered. Risperidone also appeared to impair maternal behavior in that offspring body weight gain and survival (from Day 1 to 4 of lactation) were reduced in offspring born to control but reared by drug-treated dams. All of these effects occurred at 5 mg/kg which is 3 times the oral MRHD based on mg/m^2 and the only dose tested in the study.

Subcutaneous administration of the delivery system to pregnant rats and rabbits during the period of organogenesis caused maternal toxicity (decreased body weight, weight gain and food intake), post-implantation loss, decrease in number of live fetuses and decrease in fetal weight at doses that are 52 (rat), and 43 (rabbit) times the delivery system amount present in monthly 120 mg risperidone subcutaneous injectable suspension based on mg/m^2body surface area. Developmental toxicity in both rat and rabbit included skeletal and visceral malformations at doses 35 (rat), and 43 (rabbit) times the delivery system amount present in monthly 120 mg risperidone subcutaneous injectable suspension based on mg/m^2body surface area. The NOAEL dose for these effects in both species is 17 times the delivery system amount present in monthly 120 mg risperidone subcutaneous injectable suspension based on mg/m^2body surface area. These effects could be related to N-methyl-2-pyrrolidone (NMP), an excipient present in the delivery system. In published animal developmental toxicity studies, NMP administered orally daily to pregnant rats during organogenesis produced developmental toxicity below maternally toxic levels and resulted in dose-dependent decrease in fetal body weights, increased incidence of post-implantation loss, incomplete ossification and increased incidence of external, visceral and skeletal malformations. These toxicities occurred at doses that are ~3 to 12 times the NMP amount present in monthly 120 mg risperidone subcutaneous injectable suspension based on mg/m^2body surface area.

8.2 Lactation

Risk Summary

Limited data from published literature reports the presence of risperidone and its metabolite, 9-hydroxyrisperidone, in human breast milk at relative infant dose ranging between 2.3 and 4.7% of the maternal weight-adjusted dosage. There are reports of sedation, failure to thrive, jitteriness, and extrapyramidal symptoms (tremors and abnormal muscle movements) in breastfed infants exposed to risperidone (see Clinical Considerations).There is no information on the effects of risperidone on milk production. The developmental and health benefits of breastfeeding should be considered along with the mother's clinical need for PERSERIS and any potential adverse effects on the breastfed child from PERSERIS or from the mother's underlying condition.

Clinical Considerations

Infants exposed to PERSERIS through breastmilk should be monitored for excess sedation, failure to thrive, jitteriness, and extrapyramidal symptoms (tremors and abnormal muscle movements).

8.3 Females and Males of Reproductive Potential

Infertility

Females

Based on the pharmacologic action of risperidone (D2receptor antagonism), treatment with PERSERIS may result in an increase in serum prolactin levels, which may lead to a reversible reduction in fertility in females of reproductive potential [see Warnings and Precautions (5.6) and Nonclinical Toxicology (13.1)].

8.4 Pediatric Use

Safety and effectiveness of PERSERIS have not been established in pediatric patients.

8.5 Geriatric Use

Clinical studies of PERSERIS in the treatment of schizophrenia did not include patients aged 65 and older to determine whether or not they respond differently from younger patients.

In general, dose selection for an elderly patient should be cautious, usually starting at the low end of the dosing range, reflecting the greater frequency of decreased hepatic, renal, or cardiac function, and of concomitant disease or other drug therapy.

Elderly patients with dementia-related psychosis treated with PERSERIS are at an increased risk of death compared to placebo. PERSERIS is not approved for the treatment of patients with dementia related psychosis [see Boxed Warningand Warnings and Precautions (5.1, 5.2)] .

8.6 Renal Impairment

In patients with renal impairment, carefully titrate with oral risperidone (up to at least 3 mg) before initiating treatment with PERSERIS [see Dosage and Administration (2.2) and Clinical Pharmacology (12.3)] .

PERSERIS was not studied in patients with renal impairment, however, such effect has been investigated with oral risperidone.

8.7 Hepatic Impairment

In patients with hepatic impairment, carefully titrate with oral risperidone (up to at least 3 mg) before initiating treatment with PERSERIS [see Dosage and Administration (2.2) and Clinical Pharmacology (12.3)] .

PERSERIS was not studied in patients with hepatic impairment, however, such effect has been investigated with oral risperidone.

8.8 Patients with Parkinson's Disease or Dementia with Lewy Bodies

Patients with Parkinson's disease or dementia with Lewy bodies can experience increased sensitivity to risperidone. Manifestations can include confusion, obtundation, postural instability with frequent falls, extrapyramidal symptoms, and clinical features consistent with neuroleptic malignant syndrome.

10 OVERDOSAGE

10.1 Human Experience

No cases of overdose were reported in premarketing studies with PERSERIS. Because PERSERIS is to be administered by healthcare providers, the potential for overdosage by patients is low.

10.2 Management of Overdosage

In case of overdosage, consult a Poison Control Center at 1-800-222-1222.

In case of acute overdosage, establish and maintain an airway and ensure adequate oxygenation and ventilation. Cardiovascular monitoring should commence immediately and should include continuous electrocardiographic monitoring to detect possible arrhythmias. If antiarrhythmic therapy is administered, disopyramide, procainamide, and quinidine carry a theoretical hazard of QT prolonging effects that might be additive to those of risperidone. Similarly, it is reasonable to expect that the alpha-blocking properties of bretylium might be additive to those of risperidone, resulting in problematic hypotension.

There is no specific antidote to risperidone. Appropriate supportive measures should be instituted. Hypotension and circulatory collapse should be treated with appropriate measures, such as intravenous fluids and/or sympathomimetic agents (epinephrine and dopamine should not be used, since beta stimulation may worsen hypotension in the setting of risperidone-induced alpha blockade). In cases of severe extrapyramidal symptoms, anticholinergic medication should be administered. Close medical supervision and monitoring should continue until the patient recovers.

Consider the long-acting nature of PERSERIS when assessing treatment needs and recovery.

11 DESCRIPTION

PERSERIS contains risperidone, an atypical antipsychotic. Risperidone belongs to the chemical class of benzisoxazole derivatives. The chemical designation 3-[2-[4-(6-fluoro-1,2-benzoxazol-3-yl) piperidin-1-yl] ethyl]-2-methyl-6,7,8,9-tetrahydropyrido[1,2-a] pyrimidin-4-one. Its molecular formula is C23H27FN4O2and its molecular weight is 410.5 g/mol.

The structural formula is:

Risperidone is a white to off-white powder. It is practically insoluble in water and soluble in methanol and 0.1 N HCl.

PERSERIS is available as a sterile two-syringe mixing system: a liquid syringe prefilled with the delivery system (colorless to yellow solution), and a powder syringe prefilled with risperidone (white to yellow).

PERSERIS for extended release injectable suspension, for subcutaneous use, is available in 90 mg and 120 mg risperidone strengths. The quantitative composition is provided below (Table 6).

Table 6 PERSERIS Constituted Product Delivered Mass
Component | PERSERIS 90 mg | PERSERIS 120 mg
Risperidone | 90 mg | 120 mg
PLGH* | 228 mg | 304 mg
N-methyl-pyrrolidine | 282 mg | 376 mg
Total mass | 600 mg | 800 mg
Total volume | 0.6 mL | 0.8 mL
*PLGH poly D,L(lactide co-glycolide); 80:20 molar ratio of lactide to glycolide

12 CLINICAL PHARMACOLOGY

12.1 Mechanism of Action

The mechanism of action of risperidone, in schizophrenia, is unclear. The drug's therapeutic activity in schizophrenia could be mediated through a combination of dopamine Type 2 (D2) and serotonin Type 2 (5HT2) receptor antagonism. The clinical effect from risperidone results from the combined concentrations of risperidone and its major metabolite, 9-hydroxyrisperidone (paliperidone) [see Clinical Pharmacology (12.3)] . Antagonism at receptors other than D2and 5HT2may explain some of the other effects of risperidone.

12.2 Pharmacodynamics

Risperidone is a monoaminergic antagonist with high affinity (Ki of 0.12 to 7.3 nM) for the serotonin Type 2 (5HT2), dopamine Type 2 (D2), α1and α2 adrenergic, and H1histaminergic receptors. Risperidone showed low to moderate affinity (Ki of 47 to 253 nM) for the serotonin 5HT1C, 5HT1D, and 5HT1Areceptors, weak affinity (Ki of 620 to 800 nM) for the dopamine D1and haloperidol-sensitive sigma site, and no affinity (when tested at concentrations > 10^-5M) for cholinergic muscarinic or β1and β2adrenergic receptors.

12.3 Pharmacokinetics

The pharmacokinetics of risperidone and total active moiety following subcutaneous injection of PERSERIS was evaluated in patients with clinically stable schizophrenia after single doses (60 mg, 90 mg, and 120 mg) (n = 101) and repeated doses [60 mg, 90 mg, 120 mg, 180 mg (1.5 times the maximum recommended dosage of PERSERIS)] (n = 68) separated by 28 days for up to 4 doses following oral risperidone.

Plasma concentrations of risperidone, 9-hydroxyrisperidone and total active moiety approached steady-state levels after the first dose of PERSERIS. Mean accumulation ratios for risperidone ranged from 1.2 to 1.7 based on mean area under the curve (AUC), and from 0.9 to 1.3 based on overall mean peak plasma concentrations (overall Cmax), indicating no to modest accumulation. For 9-hydroxyrisperidone, accumulation ratios ranged from 1.2 to 1.6 (AUC) and 0.99 to 1.3 (overall Cmax). For total active moiety, accumulation ratios ranged from 1.2 to 1.6 (AUCtau) and 0.97 to 1.3 (overall Cmax).

Following multiple doses of PERSERIS, plasma exposure (AUCtauand Cmax) of risperidone, 9-hydroxyrisperidone, and total active moiety increased in an approximately dose proportional manner over the dose range of 60 to 120 mg. At steady-state, a 2-fold increase in dose resulted in a 1.7-fold increase in Cmax(6.33 to 10.9 ng/mL) and AUCtau(2262 to 3891 ng*hr/mL) for risperidone. For 9-hydroxyrisperidone, a 2-fold increase in dose resulted in a 2.1-fold increase in Cmax(13.7 to 28.9 ng/mL) and 2-fold increase in AUCtau(5706 to 11658 ng*hr/mL). For total active moiety, a 2-fold increase in dose resulted in a 2.0-fold increase in Cmax(19.6 to 38.5 ng/mL) and a 1.9-fold increase in AUCtau(8102 to 15370 ng*hr/mL).

Plasma exposures at steady-state were compared between oral risperidone and PERSERIS. The average plasma concentrations (Cavg) of total active moiety were 18.3 ng/mL and 18.1 ng/mL for 3 mg oral risperidone and 90 mg PERSERIS, respectively. The Cavgof total active moiety were 25.2 ng/mL and 22.9 ng/mL for 4 mg oral risperidone and 120 mg PERSERIS, respectively.

Absorption

PERSERIS contains risperidone in a liquid delivery system. Following subcutaneous injection, it forms a depot that provides sustained plasma levels of risperidone over the monthly dosing interval.

After single subcutaneous injection, PERSERIS shows two absorption peaks for risperidone in plasma. The first peak of risperidone occurs with a Tmaxof 4 to 6 hours and is due to an initial release of the drug during the depot formation process. A second peak of risperidone is observed at 10 to 14 days post-dose and is associated with the slow release of risperidone from the subcutaneous depot. The first and second peaks of risperidone are of similar magnitude. For both 9-hydroxyrisperidone and total active moiety, the median Tmaxof the first peak ranges from 4 to 48 hours and the second peak ranges from 7 to 11 days.

Distribution

Following a subcutaneous injection of PERSERIS, the apparent volume of distribution is large. The extensively large values are because PERSERIS is administered as a depot injection. Risperidone is bound to albumin and α1-acid glycoprotein. The plasma protein binding of risperidone is approximately 90%, and that of its major metabolite, 9-hydroxyrisperidone, is 77%. Neither risperidone nor 9-hydroxyrisperidone displaces each other from plasma binding sites.

Elimination

Metabolism

Risperidone is extensively metabolized in the liver. The main metabolic pathway is through hydroxylation of risperidone to 9-hydroxyrisperidone by the enzyme cytochrome CYP2D6 with minor contribution by CYP3A4. A minor metabolic pathway is through N-dealkylation. The main metabolite, 9-hydroxyrisperidone, has similar pharmacological activity as risperidone. Consequently, the clinical effect of the drug results from the combined concentrations of risperidone plus 9-hydroxyrisperidone).

CYP2D6, is the enzyme responsible for metabolism of many neuroleptics, antidepressants, antiarrhythmics, and other drugs. CYP2D6 is subject to genetic polymorphism (about 6 to 8% of Caucasians, and a very low percentage of Asians, have little or no activity and are “poor metabolizers”) and to inhibition by a variety of substrates and some non-substrates, notably quinidine. Extensive CYP2D6 metabolizers convert risperidone rapidly into 9-hydroxyrisperidone, whereas poor CYP2D6 metabolizers convert it much more slowly. Plasma exposure to total active moiety was similar in CYP2D6 extensive, intermediate and poor metabolizers following subcutaneous injection with PERSERIS, supporting no need for dose adjustment based on genotype of CYP2D6.

Excretion

Risperidone and its metabolites are eliminated via the urine and, to a much lesser extent, via the feces. As illustrated by a mass balance study of a single 1 mg oral dose of^14C-risperidone administered as solution to 3 healthy male volunteers, total recovery of radioactivity at 1 week was 84%, including 70% in the urine and 14% in the feces.

Following a single subcutaneous injection of PERSERIS, the apparent terminal half-life of risperidone ranges between 9 and 11 days on average. This half-life is related to the slow release of risperidone from the subcutaneous depot and subsequent absorption of risperidone into the systemic circulation. The mean apparent terminal half-life ranges between 8 to 9 days for both 9-hydroxyrisperidone and total active moiety.

Drug Interaction Studies

No specific drug interaction studies have been performed with PERSERIS. The drug interaction data provided in this section is based on studies with oral risperidone. Effects of other drugs on the exposures of risperidone, 9-hydroxyrisperidone and total active moiety as well as the effects of risperidone on the exposures of other drugs is summarized below.

Effects of Other Drugs on Risperidone, 9-hydroxyrisperidone and Total Active Moiety Pharmacokinetics

Strong CYP2D6 Inhibitors (Fluoxetine and Paroxetine)

Fluoxetine (20 mg once daily) and paroxetine (20 mg once daily), potent CYP2D6 inhibitors, have been shown to increase the plasma concentration of risperidone by 2.5 to 2.8 folds and 3 to 9 folds, respectively. Fluoxetine did not affect the plasma concentration of 9-hydroxyrisperidone. Paroxetine lowered the concentration of 9-hydroxyrisperidone by about 10%. The effects of discontinuation of concomitant fluoxetine or paroxetine therapy on the pharmacokinetics of risperidone and 9-hydroxyrisperidone have not been studied.

Moderate CYP3A4 Inhibitor (Erythromycin)

There were no significant interactions between oral risperidone and erythromycin, a moderate CYP3A4 inhibitor.

Strong CYP3A4 Inducer (Carbamazepine)

Carbamazepine co-administration with oral risperidone decreased the steady-state plasma concentrations of risperidone and 9-hydroxyrisperidone by about 50%. Plasma concentrations of carbamazepine did not appear to be affected. Co-administration of other known CYP3A4 enzyme inducers (e.g., phenytoin, rifampin, and phenobarbital) with risperidone may cause similar decreases in the combined plasma concentrations of risperidone and 9-hydroxyrisperidone, which could lead to decreased efficacy of PERSERIS.

Amitriptyline, Cimetidine, Ranitidine, Clozapine, Topiramate

Clinically meaningful pharmacokinetic interaction between PERSERIS and other drugs, such as amitriptyline, cimetidine, ranitidine and clozapine, is not expected.

- Amitriptyline did not affect the pharmacokinetics of risperidone or of risperidone and 9-hydroxyrisperidone combined following concomitant administration with oral risperidone.
- Cimetidine and ranitidine increased the bioavailability of oral risperidone by 64% and 26%, respectively. However, cimetidine did not affect the AUC of risperidone and 9-hydroxyrisperidone combined, whereas ranitidine increased the AUC of risperidone and 9-hydroxyrisperidone combined by 20%.
- Chronic administration of clozapine with oral risperidone have shown to affect the clearance of risperidone, however, clinical relevance is unknown.
- There was no clinically relevant effect of oral risperidone (1 to 6 mg/day) on the pharmacokinetics of topiramate 400 mg/day.

Effects of Oral Risperidone on Pharmacokinetics of Other Drugs

Lithium

Repeated doses of oral risperidone (3 mg twice daily) did not affect the exposure (AUC) or peak plasma concentrations (Cmax) of lithium (n = 13).

Valproate

Repeated doses of oral risperidone (4 mg once daily) did not affect the pre-dose or average plasma concentrations and exposure (AUC) of valproate (1000 mg/day in three divided doses) compared to placebo (n = 21). However, there was a 20% increase in valproate peak plasma concentration (Cmax) after concomitant administration of oral risperidone.

Topiramate

Oral risperidone administered at doses from 1 to 6 mg/day concomitantly with topiramate 400 mg/day resulted in a 23% decrease in risperidone Cmaxand a 33% decrease in risperidone AUC0-12hour at steady state. Minimal reductions in the exposure to risperidone and 9-hydroxyrisperidone combined, and no change for 9-hydroxyrisperidone were observed. This interaction is unlikely to be of clinical significance. There was no clinically relevant effect of oral risperidone on the pharmacokinetics of topiramate.

Digoxin

Oral risperidone (0.25 mg twice daily) did not show a clinically relevant effect on the pharmacokinetics of digoxin.

CYP2D6 Substrates (Donepezil and Galantamine)

In vitrostudies indicate that risperidone is a relatively weak inhibitor of CYP2D6. Therefore, PERSERIS is not expected to substantially inhibit the clearance of drugs that are metabolized by this enzymatic pathway. In drug interaction studies, oral risperidone did not significantly affect the pharmacokinetics of donepezil and galantamine, which are metabolized by CYP2D6.

Specific Populations

Based on population pharmacokinetic analyses, age, sex and race do not have a clinically meaningful effect on the pharmacokinetics of PERSERIS.

Renal Impairment

PERSERIS was not studied in patients with renal impairment, however, such effect has been investigated with oral risperidone. In patients with moderate to severe renal disease treated with oral risperidone, the apparent clearance (CL/F) of total active moiety was decreased by 60% in patients with moderate to severe renal disease compared with young healthy subjects [see Use in Specific Populations (8.6)].

Hepatic Impairment

The effect of hepatic impairment on the pharmacokinetics of PERSERIS has not been studied.

The effect of hepatic impairment on the pharmacokinetics of oral risperidone has been evaluated in a dedicated phase I study. While the pharmacokinetics of risperidone in subjects with liver disease were comparable to those in young healthy subjects, the mean free fraction of risperidone in plasma was increased by about 35% because of the diminished concentration of both albumin and α1-acid glycoprotein [see Use in Specific Populations (8.7)] .

13 NONCLINICAL TOXICOLOGY

13.1 Carcinogenesis, Mutagenesis, Impairment of Fertility

Carcinogenesis

No carcinogenicity studies were conducted with subcutaneous risperidone suspension. Carcinogenicity studies were conducted with oral risperidone in mice and rats. Risperidone was administered in the diet at doses of 0.63, 2.5, and 10 mg/kg for 18 months to mice and for 25 months to rats. These doses are equivalent to approximately 0.2, 0.75, and 3 times (mice) and 0.4, 1.5, and 6 times (rats) the oral MHRD of 16 mg/day, based on a mg/m^2body surface area. A maximum tolerated dose was not achieved in male mice. There were statistically significant increases in pituitary gland adenomas, endocrine pancreas adenomas, and mammary gland adenocarcinomas. The table below summarizes the multiples of the human oral dose on a mg/m^2 (mg/kg) basis at which these tumors occurred.

Table 7 Summary of Tumor Occurrence at the Multiples of the Human Dose on a mg/m^2(mg/kg) Basis with Oral Risperidone Dosing
 |  |  | Multiples of Maximum Human Oral Dose in mg/m^2 (mg/kg)
Tumor Type | Species | Sex | Lowest Effect Level | Highest No-Effect Level
Pituitary adenomas | mouse | Female | 0.75 (9.4) | 0.2 (2.4)
Endocrine pancreas adenomas | rat | Male | 1.5 (9.4) | 0.4 (2.4)
Mammary gland adenocarcinomas | mouse | Female | 0.2 (2.4) | None
 | rat | Female | 0.4 (2.4) | None
 | rat | Male | 6 (37.5) | 1.5 (9.4)
Mammary gland neoplasm, Total | rat | Male | 1.5 (9.4) | 0.4 (2.4)

Antipsychotic drugs have been shown to chronically elevate prolactin levels in rodents. Serum prolactin levels were not measured during the risperidone carcinogenicity studies; however, measurements during subchronic toxicity studies showed that risperidone elevated serum prolactin levels 5- to 6-fold in mice and rats at the same doses used in the carcinogenicity studies. An increase in mammary, pituitary, and endocrine pancreas neoplasms has been found in rodents after chronic administration of other antipsychotic drugs and is considered to be prolactin-mediated. The relevance for human risk of the findings of prolactin-mediated endocrine tumors in rodents is unclear [see Warnings and Precautions (5.6)] .

Mutagenesis

No evidence of mutagenic or clastogenic potential for risperidone was found in the in vitrotests of Ames gene mutation, the mouse lymphoma assay, rat hepatocyte DNA-repair assay, the chromosomal aberration test in human lymphocytes, Chinese hamster ovary cells, or in the in vivooral micronucleus test in mice and the sex-linked recessive lethal test in Drosophila.

No evidence of mutagenic potential was observed with risperidone subcutaneous injectable suspension or its delivery system alone at doses of 150 mg/kg risperidone or 943 mg/kg delivery system in an in vivomicronucleus test in rats. The safety margins of risperidone were 12 to 19 times the maximum monthly plasma risperidone concentration observed for humans at the monthly MRHD of 120 mg risperidone based on plasma exposure, and 13 times the delivery system amount present in monthly 120 mg risperidone.

Impairment of Fertility

No mating and fertility studies were conducted with subcutaneous risperidone suspension. Oral risperidone (0.16 to 5 mg/kg) impaired mating, but not fertility, in rat reproductive studies at doses 0.1 to 3 times the oral maximum recommended human dose (MRHD), of 16 mg/day based on mg/m^2body surface area. The effect appeared to be in females, since impaired mating behavior was not noted in the male fertility study. In a subchronic study in Beagle dogs in which risperidone was administered orally at doses of 0.31 to 5 mg/kg, sperm motility and concentration were decreased at doses 0.6 to 10 times the oral MRHD based on mg/m^2body surface area. Dose-related decreases were also noted in serum testosterone at the same doses. Serum testosterone and sperm parameters partially recovered, but remained decreased after treatment was discontinued. A no-effect dose could not be determined in either rat or dog.

Subcutaneous administration of the delivery system to rats had no effect on fertility parameters in either sex up to a dose that is 17 (delivery system), and 23 (N-methyl-2-pyrrolidone) times the amount present in monthly 120 mg risperidone subcutaneous injectable suspension based on mg/m^2body surface area, respectively.

14 CLINICAL STUDIES

Efficacy for PERSERIS was demonstrated in an 8-week, randomized, double-blind, placebo-controlled study (Study 1, NCT #02109562). The study evaluated the efficacy, safety and tolerability of PERSERIS (90 and 120 mg subcutaneous every 4-weeks) compared with placebo in adults (age 18- to 55-years, inclusive) experiencing acute exacerbations of schizophrenia. Patients were required to have a Positive and Negative Syndrome Scale (PANSS) total score of 80- to 120-inclusive (moderate to severely ill) at the screening visit, occurring 3- to 8-days before the start of double-blind treatment, without an improvement in the PANSS total score of ≥ 20% between screening and the first dosing day.

At the screening visit, all patients received two doses of 0.25 mg oral risperidone 24-hours apart to establish tolerability. Patients were then placed in an inpatient setting, if not already hospitalized, and tapered off their current oral antipsychotic medication (if they were taking one) over a period of 3- to 8-days. Patients were randomized to receive 2 doses of subcutaneous PERSERIS (90 mg or 120 mg) or placebo 28-days apart (on Day 1 and Day 29). No supplemental oral risperidone was permitted during the study.

The primary endpoint was the change in PANSS total score from baseline to end of study (Day 57). Both PERSERIS 90 and 120 mg doses demonstrated a statistically significant improvement compared with placebo based on the primary endpoint (Table 8). The results at each scheduled visit are displayed in Figure 14.

Characteristics of the patient population were balanced across the treatment groups. The mean baseline PANSS total score ranged from 94 to 96 across the groups. Most patients were male (74 to 83% per group), and the mean ages were 40 to 43 in each group. Most patients in this study were black or African American (71 to 75% per group). Of the 354 patients randomized to treatment, 337 were included in the intent-to-treat (ITT) population, and 259 (73%) completed the study.

Subgroup analyses by gender, age, and race did not suggest any clear evidence of differential responsiveness to PERSERIS.

Table 8 Primary Efficacy Analysis Results for Study 1
 |  | Primary Efficacy Measure: PANSS
Treatment Group | N (# ITT patients) | Mean Baseline Score (SD) | LS Mean Change from Baseline (SE) | Placebo-subtracted Differencea (95% CI)
PERSERIS 90 mg* | 111 | 95.5 (9.23) | -19.86 (1.56) | -6.50 (-10.87, -2.13)*
PERSERIS 120 mg* | 114 | 94.9 (8.09) | -23.61 (1.58) | -10.24 (-14.64, -5.85)*
Placebo | 112 | 94.1 (8.89) | -13.37 (1.58) | --
ITT: intent-to-treat; SD: standard deviation; SE: standard error; LS Mean: least-squares mean; CI: unadjusted confidence interval
ªDifference (drug minus placebo) in least-squares mean change from baseline
*Doses that are statistically significantly superior to placebo

Figure 14. Least Square Mean Change from Baseline (+/- Standard Error) in PANSS Total Scores by Days

The secondary efficacy endpoint was defined as the CGI-S score at Day 57. Both PERSERIS treatment groups demonstrated statistically significantly better CGI-S scores versus placebo.

16 HOW SUPPLIED/STORAGE AND HANDLING

PERSERIS (risperidone) for extended-release injectable suspension, for subcutaneous use is, when fully mixed a viscous suspension that, varies from white to yellow-green and is available in dosage strengths of 90 mg and 120 mg.

PERSERIS 90 mg is supplied in a single-dose kit, packaged in a carton (NDC 12496-0090-1), containing the following:

- One pouch with a sterile syringe (labelled ‘P’) prefilled with risperidone powder
- One pouch with a sterile syringe (labelled ‘L’) prefilled with the delivery system, and desiccant.
- One 18-gauge, 5/8-inch sterile safety needle.

PERSERIS 120 mg is supplied in a single-dose kit, packaged in a carton (NDC 12496-0120-1), containing the following:

- One pouch with a sterile syringe (labelled ‘P') prefilled with risperidone powder.
- One pouch with a sterile syringe (labelled ‘L') prefilled with the delivery system, and desiccant.
- One 18-gauge, 5/8-inch sterile safety needle.

Storage and Handling

Store in refrigerator at 2°C to 8°C (36°F to 46°F). Allow PERSERIS kit to come to room temperature, 20°C to 25°C (68°F to 77°F), for at least 15 minutes prior to mixing.

PERSERIS may be stored in its unopened original packaging at room temperature, 20°C to 25°C (68°F to 77°F), for up to 30 days prior to administration. After removal from the refrigerator, use PERSERIS within 30 days or discard.

17 PATIENT COUNSELING INFORMATION

General Instructions

Advise patients not to rub or massage the injection site and to be aware of the placement of any belts or clothing waistbands, sleeves, cuffs, or other parts of clothing [see Dosage and Administration (2.4)] .

Neuroleptic Malignant Syndrome

Counsel patients about a potentially fatal adverse reaction, Neuroleptic Malignant Syndrome (NMS), that has been reported in association with administration of antipsychotic drugs. Advise patients, family members, or caregivers to contact the healthcare provider or report to the emergency room if they experience signs and symptoms of NMS [see Warnings and Precautions (5.3)] .

Tardive Dyskinesia

Counsel patients on the signs and symptoms of tardive dyskinesia and to contact their healthcare provider if these abnormal movements occur [see Warnings and Precautions (5.4)] .

Metabolic Changes

Educate patients about the risk of metabolic changes, how to recognize symptoms of hyperglycemia and diabetes mellitus, and the need for specific monitoring, including blood glucose, lipids, and weight [see Warnings and Precautions (5.5)] .

Hyperprolactinemia

Counsel patients on signs and symptoms of hyperprolactinemia that may be associated with chronic use of PERSERIS. Advise them to seek medical attention if they experience any of the following: amenorrhea or galactorrhea in females, erectile dysfunction or gynecomastia in males [see Warnings and Precautions (5.6)] .

Orthostatic Hypotension and Syncope

Educate patients of the risk of orthostatic hypotension and syncope, particularly at the time of initiating treatment, re-initiating treatment, or increasing the dose [see Warnings and Precautions (5.7)].

Leukopenia/Neutropenia

Advise patients with a pre-existing low WBC or a history of drug induced leukopenia/neutropenia they should have their CBC monitored while taking PERSERIS [see Warnings and Precautions (5.9)] .

Potential for Cognitive and Motor Impairment

Inform patients that PERSERIS has the potential to impair judgment, thinking, and motor skills. Caution patients about performing activities requiring mental alertness, such as operating hazardous machinery or operating a motor vehicle, until they are reasonably certain that PERSERIS does not affect them adversely [see Warnings and Precautions (5.10)] .

Priapism

Advise patients of the possibility of painful or prolonged penile erections (priapism). Instruct the patient to seek immediate medical attention in the event of priapism [Warnings and Precautions (5.13)] .

Heat Exposure and Dehydration

Educate patients regarding appropriate care in avoiding overheating and dehydration [see Warnings and Precautions (5.14)].

Concomitant Medication

Advise patients to inform their physicians if they are taking, or plan to take, any prescription or over-the-counter drugs, since there is a potential for interaction [see Drug Interactions (7)] .

Alcohol

Advise patients to avoid alcohol during treatment with PERSERIS [see Drug Interactions (7.1)] .

Pregnancy

Advise patients to notify their healthcare provider if they become pregnant or intend to become pregnant during treatment with PERSERIS. Advise patients that PERSERIS may cause extrapyramidal and/or withdrawal symptoms (agitation, hypertonia, hypotonia, tremor, somnolence, respiratory distress, and feeding disorder) in a neonate. Advise patients that there is a pregnancy registry that monitors pregnancy outcomes in women exposed to PERSERIS during pregnancy [see Use in Specific Populations (8.1)] .

Lactation

Advise breastfeeding women using PERSERIS to monitor infants for somnolence, failure to thrive, jitteriness, and extrapyramidal symptoms (tremors and abnormal muscle movements) and to seek medical care if they notice these signs [see Use in Specific Populations (8.2)] .

Infertility

Advise females of reproductive potential that PERSERIS may impair fertility due to an increase in serum prolactin levels. The effects on fertility are reversible [see Use in Specific Populations (8.3)].

Manufactured for:

Indivior Inc., North Chesterfield, VA 23235.

© 2025, Indivior UK Limited. All Rights Reserved.

PERSERIS is a registered trademark of Indivior UK Limited.

Powder syringe manufactured by Patheon Manufacturing Services, Greenville, NC 27834.

Liquid syringe manufactured by Curia, Burlington, MA 01803.

INSTRUCTIONS FOR USE

PERSERIS® (risperidone) for extended-release injectable suspension

90 mg or 120 mg, sterile, single dose

For subcutaneous injection only.
Do not administer by any other route.

IMPORTANT INFORMATION:

- To be administered by a healthcare professional only.
- Please read the instructions carefully before handling this product.
- Allow package to come to room temperature for at least 15 minutes prior to preparation.
- Only prepare medication when you are ready to administer the dose.
- As a universal precaution, always wear gloves.

1 CHECK CONTENTS

- One Liquid Syringe () pre-filled with the delivery system – Inspect liquid solution for foreign particles. This is the syringe you will use to inject the patient.
- One Powder Syringe() prefilled with Risperidone powder – Inspect syringe for consistency of powder color and for foreign particles.
- One sterile 18-gauge, 5/8-inch safety needle
- Parenteral drug products should always be inspected visually for particulate matter and discoloration prior to administration, whenever solution and container permit.

2 TAP POWDER SYRINGE

- Hold the Powder Syringeupright and tap the barrel of the syringe to dislodge the packed powder.

Powder can become packed during shipping.

3 UNCAP LIQUID AND POWDER SYRINGES

- Remove the cap from the Liquid Syringe, then remove the cap from the Powder Syringe.

Holding both syringes in your non-dominant hand can help with this step.

4 CONNECT THE SYRINGES

- Place the Liquid Syringeon top of the Powder Syringe(to prevent powder spillage) and connect the syringes by twisting approximately ¾ turn. Do not over tighten.

Keep your fingers off the plungers during this step to avoid spillage of the medication.

5 MIX THE PRODUCT
Failure to fully mix the medication could result in incorrect dosage.
Premixing:

- Transfer the contents of the Liquid Syringeinto the Powder Syringe.
- Gently push the Powder Syringeplunger until you feel resistance (to wet powder and avoid compacting).
- Repeat this gentle back-and-forth process for 5 Cycles.
  Complete mixing:
- Continue mixing the syringes for an additional 55 Cycles.
- This mixing can be more vigorous than when premixing.
  When fully mixed, the product should be a cloudy suspension that is uniform in color. It can vary from white to yellow-green in color. If you see any clear areas in the mixture, continue to mix until the distribution of the color is uniform. The product is designed to deliver risperidone 90 mg or 120 mg.
  Graphic to the right illustrates a correct full cycle.

6 PREPARE INJECTION SYRINGE
Failure to aspirate the liquid from the Powder Syringemay result in incorrect dosage.

- First, transfer all contents into the Liquid Syringe.
- Next, perform the following actions SIMULTANEOUSLY:
  - maintain slight pressure on the Powder Syringeplunger and
  - pull back gentlyon the Liquid Syringeplunger while twisting the syringes apart.
- Finally, attach the safety needle by twisting until finger tight.
  Check that medication is uniform in color and free from foreign particles.

PERSERIS®
Instructions for Use

7 PREPARE THE SUBCUTANEOUS INJECTION SITE

- This medication is to be injected subcutaneously in the abdomen (see figure) or back of upper arm (see figure).
- Choose an injection site with adequate subcutaneous tissue that is free of skin conditions (e.g. nodules, lesions, excessive pigment).
- Do notinject into an area where the skin is irritated, reddened, bruised, infected or scarred in any way.
- Clean the injection site well with an alcohol pad.

To help minimize irritation, rotate injection sites following a pattern similar to the illustration. If you want to use the same injection site, make sure it is not the same spot on the injection site you used the last time.

8 REMOVE EXCESS AIR FROM SYRINGE

- Hold the syringe upright for several seconds to allow air bubbles to rise.
- Remove needle cover and slowly depress the plunger to push out the excess air from the syringe.
- If medication is seen at the needle tip, pull back slightly on the plunger to prevent medication spillage.

Due to the viscous nature of the medication, bubbles will not rise as quickly as those in an aqueous solution.

9 PINCH INJECTION SITE

- Pinch the skin around the injection area. Be sure to pinch enough skin to accommodate the size of the needle. Lift the adipose tissue from the underlying muscle to prevent accidental intramuscular injection.

10 INJECT THE MEDICATION

- Insert needle fully into the subcutaneous tissue.
- Inject the medication slow and steady.
  PERSERIS is for subcutaneous administration only. Do not inject by any other route.
  Actual angle of injection will depend on the amount of subcutaneous tissue.

11 WITHDRAW NEEDLE

- Withdraw the needle at the same angle used for insertion and release pinched skin.

Do not rub the injection area after the injection. If there is bleeding, apply a gauze pad or bandage but use minimal pressure.

12 LOCK THE NEEDLE GUARD AND DISPOSE OF SYRINGE

- Lock the needle guard into place by pushing it against a hard surface such as a table.
- Dispose of all syringe components in a secure sharps disposal container.

13 INSTRUCT THE PATIENT

- Advise the patient that they may have a lump for several weeks that will decrease in size over time. It is important that the patient not rub or massage the injection site and to be aware of the placement of any belts, waistbands, sleeves, cuffs or other parts of clothing.

FREQUENTLY ASKED QUESTIONS
Q What is the mixture supposed to look like?
AWhen fully mixed, the product should be a cloudy suspension that is uniform in color. It can vary from white to yellow-green in color. If you see any clear areas in the mixture, continue to mix until the distribution of the color is uniform.
Q Why is it important to put the liquid syringe on top?
AThe liquid is viscous and will not fall out when placing on top. However, powder may be lost if the powder syringe is inverted, which could affect the ultimate dosage.
Q What do I do if there is residual left in the powder syringe?
AA small ring of residual powder may be observed in the end of the powder syringe barrel after mixing. This is normal. If you have followed the instructions carefully and the rest of the mixture is a cloudy suspension that is uniform in color, proceed with the injection.
Q What do I do if a foreign particle is found in either of the syringes?
ADo not use if you suspect foreign particles in either of the syringes.
Q How soon must I inject after mixing PERSERIS®?
AThis product should be used immediately following preparation.
Q Can I inject into the leg?
AThis injection is only approved for injection into the subcutaneous tissue of abdomen and back of the upper arm.
Q How do I get rid of large air gaps?
ASmall bubbles, also known as champagne bubbles, are not a problem and common with this medication. Large air gaps, however, can be minimized by pulling back on the plunger rod to pop air bubbles prior to expelling the air very slowly. Air should be expelled very carefully to avoid loss of medication.
Q Should I massage or put my finger on the injection site following the injection?
AIt is not advisable to palpate or massage the area following the injection.
Q Will the deposit be palpable?
ADepending on the patient's subcutaneous tissue, the deposit may be more or less palpable. Patients should be advised that a bump may be palpable (decreasing in size) for several weeks.

Manufactured for: Indivior Inc., North Chesterfield, VA 23235.
© 2022, Indivior UK Limited. All Rights Reserved.
PERSERIS is a registered trademark of Indivior UK Limited.
Powder syringe manufactured by Patheon Manufacturing Services, Greenville, NC 27834.
Liquid syringe manufactured by Curia, Burlington, MA 01803.

This Instructions for Use has been approved by the U.S. Food and Drug Administration.

Revised 12/2022

PACKAGE LABEL

Principal Display Panel - Perseris Kit 90 mg Carton Label

NDC 12496-0090-1

once-monthly

PERSERIS®
(risperiDONE)

for extended-release
injectable suspension

90 mg

Liquid
Syringe

+
Mix

Powder
Syringe

1 Injection

Rx only

Sterile

Single-dose only

For subcutaneous injection only. Please read complete instructions prior to use.

PACKAGE LABEL

Principal Display Panel - Perseris Kit 120 mg Carton Label

NDC 12496-0120-1

once-monthly

PERSERIS®
(risperiDONE)

for extended-release
injectable suspension

120 mg

Liquid
Syringe

+
Mix

Powder
Syringe

1 Injection

Rx only

Sterile

Single-dose only

For subcutaneous injection only. Please read complete instructions prior to use.